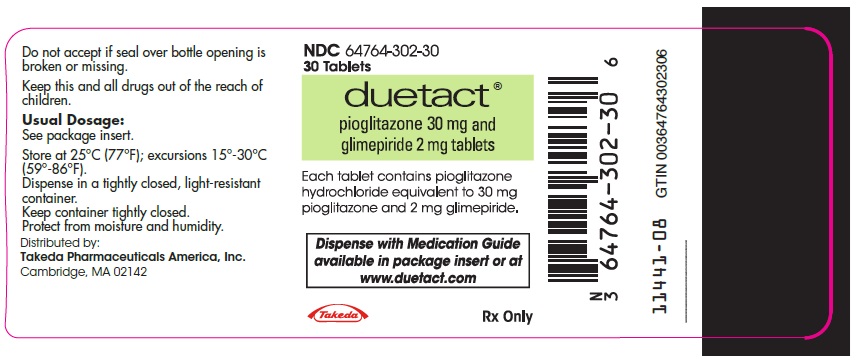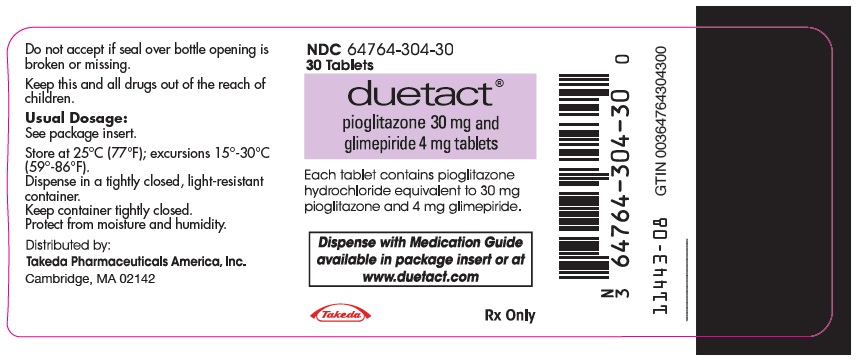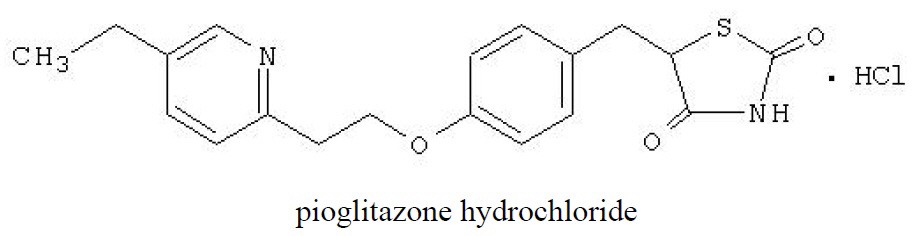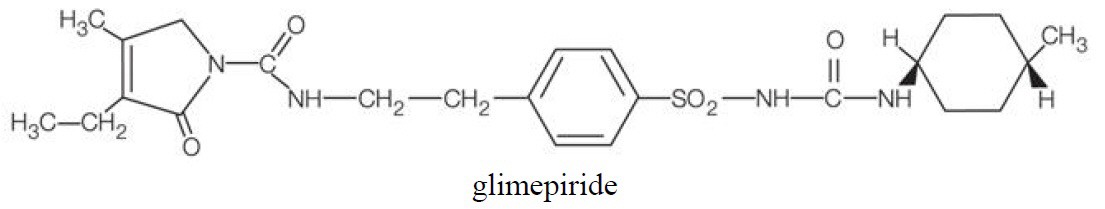 DRUG LABEL: Duetact
NDC: 64764-302 | Form: TABLET
Manufacturer: Takeda Pharmaceuticals America, Inc.
Category: prescription | Type: HUMAN PRESCRIPTION DRUG LABEL
Date: 20250327

ACTIVE INGREDIENTS: pioglitazone hydrochloride 30 mg/1 1; glimepiride 2 mg/1 1
INACTIVE INGREDIENTS: croscarmellose sodium; lactose monohydrate; magnesium stearate; HYDROXYPROPYL CELLULOSE (1600000 WAMW); polysorbate 80; microcrystalline cellulose

HIGHLIGHTS OF PRESCRIBING INFORMATION

These highlights do not include all the information needed to use DUETACT® safely and effectively. See full prescribing information for DUETACT.
DUETACT (pioglitazone and glimepiride) tablets for oral use
Initial U.S. Approval: 2006

WARNING: CONGESTIVE HEART FAILURE

See full prescribing information for complete boxed warning.

- Thiazolidinediones, including pioglitazone, which is a component of DUETACT, cause or exacerbate congestive heart failure in some patients. (5.1)
- After initiation of DUETACT, and after dose increases, monitor patients carefully for signs and symptoms of heart failure (e.g., excessive, rapid weight gain, dyspnea, and/or edema). If heart failure develops, it should be managed according to current standards of care and discontinuation or dose reduction of DUETACT must be considered. (5.1)
- DUETACT is not recommended in patients with symptomatic heart failure. (5.1)
- Initiation of DUETACT in patients with established New York Heart Association (NYHA) Class III or IV heart failure is contraindicated. (4, 5.1)

1 INDICATIONS AND USAGE

DUETACT is a thiazolidinedione and a sulfonylurea combination product indicated as an adjunct to diet and exercise to improve glycemic control in adults with type 2 diabetes mellitus when treatment with both pioglitazone and glimepiride is appropriate. (1)

Important Limitations of Use:

- Not for treatment of type 1 diabetes or diabetic ketoacidosis. (1)

2 DOSAGE AND ADMINISTRATION

- Individualize the starting dose of DUETACT based on the patient's current regimen. (2.1)
- May adjust the dosing based on effectiveness and tolerability while not exceeding the maximum recommended daily dose of pioglitazone 45 mg and glimepiride 8 mg. (2.1)
- DUETACT should be given in a single dose once daily with meals. (2.1)
- Obtain liver tests before starting DUETACT. If abnormal, use caution when treating with DUETACT, investigate the probable cause, treat (if possible) and follow appropriately. Monitoring liver tests while on DUETACT is not recommended in patients without liver disease. (5.5)

3 DOSAGE FORMS AND STRENGTHS

- Tablets: 30 mg pioglitazone/2 mg glimepiride. (3)
- Tablets: 30 mg pioglitazone/4 mg glimepiride. (3)

4 CONTRAINDICATIONS

- Initiation in patients with established New York Heart Association (NYHA) Class III or IV heart failure [see Boxed Warning]. (4)
- Use in patients with known hypersensitivity to pioglitazone, glimepiride or any other component of DUETACT. (4)
- Hypersensitivity to sulfonamide derivatives. (4)

5 WARNINGS AND PRECAUTIONS

- Congestive heart failure: Fluid retention may occur and can exacerbate or lead to congestive heart failure. Combination use with insulin and use in congestive heart failure NYHA Class I and II may increase risk. Monitor patients for signs and symptoms. (5.1)
- Hypoglycemia: May be severe. When insulin or an insulin secretagogue is used with pioglitazone, a lower dose of the insulin or insulin secretagogue may be needed to reduce the risk of hypoglycemia. (5.2)
- Hypersensitivity Reactions: Postmarketing reports for glimepiride, a component of DUETACT, include anaphylaxis, angioedema and Stevens-Johnson Syndrome. Promptly discontinue DUETACT, assess for other cases, institute appropriate monitoring and treatment, and initiate alternative treatment for diabetes. (5.3)
- Potential increased risk of cardiovascular mortality with sulfonylureas: Inform patients of risk, benefits, and treatment alternatives. (5.4)
- Hepatic effects: Postmarketing reports of hepatic failure, sometimes fatal. Causality cannot be excluded. If liver injury is detected, promptly interrupt DUETACT and assess patient for probable cause, then treat cause if possible, to resolution or stabilization. Do not restart DUETACT if liver injury is confirmed and no alternate etiology can be found. (5.5)
- Bladder cancer: May increase the risk of bladder cancer. Do not use in patients with active bladder cancer. Use caution when using in patients with a prior history of bladder cancer (5.6)
- Edema: Dose-related edema may occur. (5.7)
- Fractures: Increased incidence in female patients. Apply current standards of care for assessing and maintaining bone health. (5.8)
- Hemolytic anemia: Can occur if glucose 6-phophate dehydrogenase (GP6D) deficient. Use with caution in patients with GP6D deficiency. (5.9)
- Macular edema: Postmarketing reports. Recommend regular eye exams in all patients with diabetes according to current standards of care with prompt evaluation for acute visual changes. (5.10)
- Macrovascular outcomes: There have been no clinical studies establishing conclusive evidence of macrovascular risk reduction with DUETACT. (5.11)

6 ADVERSE REACTIONS

Most common adverse reactions (≥5%) are upper respiratory tract infection, accidental injury, and combined edema/peripheral edema. (6.1)

To report SUSPECTED ADVERSE REACTIONS, contact Takeda Pharmaceuticals America, Inc. at 1-877-TAKEDA-7 (1-877-825-3327) or FDA at 1-800-FDA-1088 or www.fda.gov/medwatch.

7 DRUG INTERACTIONS

- Strong CYP2C8 inhibitors (e.g., gemfibrozil) increase pioglitazone concentrations. Limit pioglitazone dose to 15 mg daily. (2.3, 7.1)
- CYP2C8 inducers (e.g., rifampin) may decrease pioglitazone concentrations. (7.2)
- Topiramate may decrease pioglitazone concentrations. (7.3)
- Certain medications may affect glucose metabolism, requiring DUETACT dose adjustment and close monitoring of blood glucose (7.4).
- Miconazole: Severe hypoglycemia can occur when DUETACT and oral miconazole are used concomitantly. (7.5)
- CYP2C9 interactions: Inhibitors and inducers may affect glycemic control by altering glimepiride plasma concentrations. (7.6)
- Colesevelam: Coadministration may reduce glimepiride absorption. DUETACT should be administered at least 4 hours prior to colesevelam. (2.4, 7.7)

8 USE IN SPECIFIC POPULATIONS

- Females and Males of Reproductive Potential: Advise premenopausal females of the potential for an unintended pregnancy. (8.3)
- Pediatrics: Not recommended for use in pediatric patients. (8.4)
- Geriatric or renally impaired patients: At risk for hypoglycemia with DUETACT. Use caution in dose selection and titration, and monitor closely. (8.5, 8.6)

FULL PRESCRIBING INFORMATION

WARNING: CONGESTIVE HEART FAILURE

- Thiazolidinediones, including pioglitazone, which is a component of DUETACT®, cause or exacerbate congestive heart failure in some patients [see Warnings and Precautions (5.1)].
- After initiation of DUETACT and after dose increases, monitor patients carefully for signs and symptoms of heart failure (e.g., excessive, rapid weight gain, dyspnea, and/or edema). If heart failure develops, it should be managed according to current standards of care and discontinuation or dose reduction of DUETACT must be considered [see Warnings and Precautions (5.1)].
- DUETACT is not recommended in patients with symptomatic heart failure [see Warnings and Precautions (5.1)].
- Initiation of DUETACT in patients with established New York Heart Association (NYHA) Class III or IV heart failure is contraindicated [see Contraindications (4) and Warnings and Precautions (5.1)].

1 INDICATIONS AND USAGE

DUETACT is indicated as an adjunct to diet and exercise to improve glycemic control in adults with type 2 diabetes mellitus who are already treated with a thiazolidinedione and sulfonylurea or who have inadequate glycemic control on a thiazolidinedione alone or a sulfonylurea alone [see Clinical Studies (14)].

Important Limitations of Use

Pioglitazone exerts its antihyperglycemic effect only in the presence of endogenous insulin. DUETACT should not be used to treat type 1 diabetes or diabetic ketoacidosis, as it would not be effective in these settings.

Use caution in patients with liver disease [see Warnings and Precautions (5.5)].

2 DOSAGE AND ADMINISTRATION

2.1 Recommendations for All Patients

DUETACT should be taken once daily with the first main meal.

DUETACT tablets are available as a 30 mg pioglitazone plus 2 mg glimepiride or a 30 mg pioglitazone plus 4 mg glimepiride tablet. If therapy with a combination tablet containing pioglitazone and glimepiride is considered appropriate the recommended starting dose is:

- 30 mg/2 mg or 30 mg/4 mg once daily and gradually titrated, as needed, after assessing adequacy of therapeutic response and tolerability,
- for patients inadequately controlled on glimepiride monotherapy: 30 mg/2 mg or 30 mg/4 mg once daily and gradually titrated, as needed, after assessing adequacy of therapeutic response and tolerability,
- for patients inadequately controlled on pioglitazone monotherapy: 30 mg/2 mg once daily and gradually titrated, as needed, after assessing adequacy of therapeutic response and tolerability,
- for patients who are changing from combination therapy of pioglitazone plus glimepiride as separate tablets: DUETACT should be taken at doses that are as close as possible to the dose of pioglitazone and glimepiride already being taken,
- for patients currently on a different sulfonylurea monotherapy or switching from combination therapy of pioglitazone plus a different sulfonylurea (e.g., glyburide, glipizide, chlorpropamide, tolbutamide, acetohexamide): 30 mg/2 mg once daily and adjusted after assessing adequacy of therapeutic response. Observe for hypoglycemia for one to two weeks due to the potential overlapping drug effect.
- for patients with systolic dysfunction, the lowest approved dose of DUETACT should be prescribed only after titration from 15 mg to 30 mg of pioglitazone has been safely tolerated.

After initiation of DUETACT or with dose increase, monitor patients carefully for hypoglycemia and adverse reactions related to fluid retention such as weight gain, edema, and signs and symptoms of congestive heart failure [see Boxed Warning and Warnings and Precautions (5.7)].

Liver tests (serum alanine and aspartate aminotransferases, alkaline phosphatase, and total bilirubin) should be obtained prior to initiating DUETACT. Routine periodic monitoring of liver tests during treatment with DUETACT is not recommended in patients without liver disease. Patients who have liver test abnormalities prior to initiation of DUETACT or who are found to have abnormal liver tests while taking DUETACT should be managed as described under Warnings and Precautions [see Warnings and Precautions (5.5) and Clinical Pharmacology (12.3)].

2.2 Concomitant Use with an Insulin Secretagogue or Insulin

If hypoglycemia occurs in a patient coadministered DUETACT and an insulin secretagogue, the dose of the insulin secretagogue should be reduced.

If hypoglycemia occurs in a patient coadministered DUETACT and insulin, the dose of insulin should be decreased by 10% to 25%. Further adjustments to the insulin dose should be individualized based on glycemic response.

2.3 Concomitant Use with Strong CYP2C8 Inhibitors

Coadministration of pioglitazone and gemfibrozil, a strong CYP2C8 inhibitor, increases pioglitazone exposure approximately 3-fold. Therefore, the maximum recommended dose of pioglitazone is 15 mg daily when used in combination with gemfibrozil or other strong CYP2C8 inhibitors. If gemfibrozil or other CYP2C8 inhibitors need to co-administered, patients should switch to individual components of DUETACT because the minimum dose of pioglitazone in DUETACT exceeds 15 mg [see Drug Interactions (7.1) and Clinical Pharmacology (12.3)].

2.4 Concomitant Use with Colesevelam

When colesevelam is coadministered with glimepiride, maximum plasma concentration and total exposure to glimepiride is reduced. Therefore, DUETACT should be administered at least four hours prior to colesevelam [see Drug Interactions (7.7) and Clinical Pharmacology (12.3)].

3 DOSAGE FORMS AND STRENGTHS

- 30 mg/2 mg tablet: White to off-white, round, convex tablets, debossed with "4833G" on one side and "30/2" on the other
- 30 mg/4 mg tablet: White to off-white, round, convex tablets, debossed with "4833G" on one side and "30/4" on the other

4 CONTRAINDICATIONS

- Initiation in patients with established NYHA Class III or IV heart failure [see Boxed Warning].
- Use in patients with known hypersensitivity to pioglitazone, glimepiride or any other component of DUETACT [see Warnings and Precautions (5.3)].
- Use in patients with known history of an allergic reaction to sulfonamide derivatives.

Reported hypersensitivity reactions with glimepiride include cutaneous eruptions with or without pruritus as well as more serious reactions (e.g., anaphylaxis, angioedema, Stevens-Johnson Syndrome, dyspnea) [see Warnings and Precautions (5.3) and Adverse Reactions (6.2)]

5 WARNINGS AND PRECAUTIONS

5.1 Congestive Heart Failure

Pioglitazone

Pioglitazone, like other thiazolidinediones, can cause dose-related fluid retention when used alone or in combination with other antidiabetic medications and is most common when DUETACT is used in combination with insulin. Fluid retention may lead to or exacerbate congestive heart failure. Patients should be observed for signs and symptoms of congestive heart failure. If congestive heart failure develops, it should be managed according to current standards of care and discontinuation or dose reduction of DUETACT must be considered [see Boxed Warning, Contraindications (4) and Adverse Reactions (6.1)].

5.2 Hypoglycemia

Glimepiride

All sulfonylureas, including glimepiride, a component of DUETACT, can cause severe hypoglycemia [see Adverse Reactions (6.1)]. The patient's ability to concentrate and react may be impaired as a result of hypoglycemia. These impairments may present a risk in situations where these abilities are especially important, such as driving or operating other machinery. Severe hypoglycemia can lead to unconsciousness or convulsions and may result in temporary or permanent impairment of brain function or death.

Patients must be educated to recognize and manage hypoglycemia. Use caution when initiating and increasing DUETACT doses in patients who may be predisposed to hypoglycemia (e.g., the elderly, patients with renal impairment, patients on other antidiabetic medications). Debilitated or malnourished patients and those with adrenal, pituitary, or hepatic impairment are particularly susceptible to the hypoglycemic action of glucose-lowering medications. Hypoglycemia is also more likely to occur when caloric intake is deficient, after severe or prolonged exercise, or when alcohol is ingested.

Early warning symptoms of hypoglycemia may be different or less pronounced in patients with autonomic neuropathy, the elderly, and in patients who are taking beta-adrenergic blocking medications or other sympatholytic agents. These situations may result in severe hypoglycemia before the patient is aware of the hypoglycemia.

5.3 Hypersensitivity Reactions

Glimepiride

There have been postmarketing reports of hypersensitivity reactions in patients treated with glimepiride, a component of DUETACT, including serious reactions such as anaphylaxis, angioedema, and Stevens-Johnson Syndrome. If a hypersensitivity reaction is suspected, promptly discontinue DUETACT, assess for other potential causes for the reaction, and institute alternative treatment for diabetes.

5.4 Potential Increased Risk of Cardiovascular Mortality with Sulfonylureas

Glimepiride

The administration of oral hypoglycemic drugs has been reported to be associated with increased cardiovascular mortality as compared to treatment with diet alone or diet plus insulin. This warning is based on the study conducted by the University Group Diabetes Program (UGDP), a long-term, prospective clinical trial designed to evaluate the effectiveness of glucose-lowering drugs in preventing or delaying vascular complications in patients with non-insulin-dependent diabetes. The study involved 823 patients who were randomly assigned to one of four treatment groups.

UGDP reported that patients treated for 5 to 8 years with diet plus a fixed dose of tolbutamide (1.5 grams per day) had a rate of cardiovascular mortality approximately 2.5 times that of patients treated with diet alone. A significant increase in total mortality was not observed, but the use of tolbutamide was discontinued based on the increase in cardiovascular mortality, thus limiting the opportunity for the study to show an increase in overall mortality. Despite controversy regarding the interpretation of these results, the findings of the UGDP study provide an adequate basis for this warning. The patient should be informed of the potential risks and advantages of glimepiride tablets and of alternative modes of therapy.

Although only one drug in the sulfonylurea class (tolbutamide) was included in this study, it is prudent from a safety standpoint to consider that this warning may also apply to other oral hypoglycemic drugs in this class, in view of their close similarities in mode of action and chemical structure.

5.5 Hepatic Effects

Pioglitazone

There have been postmarketing reports of fatal and non-fatal hepatic failure in patients taking pioglitazone, although the reports contain insufficient information necessary to establish the probable cause. There has been no evidence of drug-induced hepatotoxicity in the pioglitazone-controlled clinical trial database to date [see Adverse Reactions (6.1)].

Patients with type 2 diabetes may have fatty liver disease or cardiac disease with episodic congestive heart failure, both of which may cause liver test abnormalities, and they may also have other forms of liver disease, many of which can be treated or managed. Therefore, obtaining a liver test panel (serum alanine aminotransferase [ALT], aspartate aminotransferase [AST], alkaline phosphatase, and total bilirubin) and assessing the patient is recommended before initiating DUETACT therapy. In patients with abnormal liver tests, DUETACT should be initiated with caution.

Measure liver tests promptly in patients who report symptoms that may indicate liver injury, including fatigue, anorexia, right upper abdominal discomfort, dark urine or jaundice. In this clinical context, if the patient is found to have abnormal liver tests (ALT greater than 3 times the upper limit of the reference range), DUETACT treatment should be interrupted and investigation done to establish the probable cause. DUETACT should not be restarted in these patients without another explanation for the liver test abnormalities.

Patients who have serum ALT greater than three times the reference range with serum total bilirubin greater than two times the reference range without alternative etiologies are at risk for severe drug-induced liver injury and should not be restarted on DUETACT. For patients with lesser elevations of serum ALT or bilirubin and with an alternate probable cause, treatment with DUETACT can be used with caution.

5.6 Urinary Bladder Tumors

Pioglitazone

Tumors were observed in the urinary bladder of male rats in the two-year carcinogenicity study [see Nonclinical Toxicology (13.1)]. In addition, during the three year PROactive clinical trial, 14 patients out of 2605 (0.54%) randomized to pioglitazone and 5 out of 2633 (0.19%) randomized to placebo were diagnosed with bladder cancer. After excluding patients in whom exposure to study drug was less than one year at the time of diagnosis of bladder cancer, there were 6 (0.23%) cases on pioglitazone and two (0.08%) cases on placebo. After completion of the trial, a large subset of patients was observed for up to 10 additional years, with little additional exposure to pioglitazone. During the 13 years of both PROactive and observational follow-up, the occurrence of bladder cancer did not differ between patients randomized to pioglitazone or placebo (HR =1.00; [95% CI: 0.59–1.72]).

Findings regarding the risk of bladder cancer in patients exposed to pioglitazone vary among observational studies; some did not find an increased risk of bladder cancer associated with pioglitazone, while others did.

A large prospective 10-year observational cohort study conducted in the United States found no statistically significant increase in the risk of bladder cancer in diabetic patients ever exposed to pioglitazone, compared to those never exposed to pioglitazone (HR =1.06 [95% CI 0.89–1.26]).

A retrospective cohort study conducted with data from the United Kingdom found a statistically significant association between ever exposure to pioglitazone and bladder cancer (HR: 1.63; [95% CI: 1.22–2.19]).

Associations between cumulative dose or cumulative duration of exposure to pioglitazone and bladder cancer were not detected in some studies including the 10-year observational study in the U.S., but were in others. Inconsistent findings and limitations inherent in these and other studies preclude conclusive interpretations of the observational data.

Pioglitazone may be associated with an increase in the risk of urinary bladder tumors. There are insufficient data to determine whether pioglitazone is a tumor promoter for urinary bladder tumors.

Consequently, DUETACT should not be used in patients with active bladder cancer and the benefits of glycemic control versus unknown risks for cancer recurrence with DUETACT should be considered in patients with a prior history of bladder cancer.

5.7 Edema

Pioglitazone

In controlled clinical trials, edema was reported more frequently in patients treated with pioglitazone than in placebo-treated patients and is dose-related [see Adverse Reactions (6.1)]. In postmarketing experience, reports of new onset or worsening edema have been received.

DUETACT should be used with caution in patients with edema. Because thiazolidinediones, including pioglitazone, can cause fluid retention, which can exacerbate or lead to congestive heart failure, DUETACT should be used with caution in patients at risk for congestive heart failure. Patients treated with DUETACT should be monitored for signs and symptoms of congestive heart failure [see Boxed Warning, Warnings and Precautions (5.1), and Patient Counseling Information (17)].

5.8 Fractures

Pioglitazone

In PROactive (the Prospective Pioglitazone Clinical Trial in Macrovascular Events), 5238 patients with type 2 diabetes and a history of macrovascular disease were randomized to pioglitazone (N=2605), force-titrated up to 45 mg daily or placebo (N=2633) in addition to standard of care. During a mean follow-up of 34.5 months, the incidence of bone fracture in females was 5.1% (44/870) for pioglitazone versus 2.5% (23/905) for placebo. This difference was noted after the first year of treatment and persisted during the course of the study. The majority of fractures observed in female patients were nonvertebral fractures including lower limb and distal upper limb. No increase in the incidence of fracture was observed in men treated with pioglitazone (1.7%) versus placebo (2.1%). The risk of fracture should be considered in the care of patients, especially female patients, treated with DUETACT and attention should be given to assessing and maintaining bone health according to current standards of care.

5.9 Hemolytic Anemia

Glimepiride

Sulfonylureas can cause hemolytic anemia in patients with glucose 6-phosphate dehydrogenase (G6PD) deficiency. Because DUETACT contains glimepiride, which belongs to the class of sulfonylurea agents, use caution in patients with G6PD deficiency and consider the use of a nonsulfonylurea alternative. There are also postmarketing reports of hemolytic anemia in patients receiving glimepiride who did not have known G6PD deficiency [see Adverse Reactions (6.2)].

5.10 Macular Edema

Pioglitazone

Macular edema has been reported in postmarketing experience in diabetic patients who were taking pioglitazone or another thiazolidinedione. Some patients presented with blurred vision or decreased visual acuity, but others were diagnosed on routine ophthalmologic examination.

Most patients had peripheral edema at the time macular edema was diagnosed. Some patients had improvement in their macular edema after discontinuation of the thiazolidinedione.

Patients with diabetes should have regular eye exams by an ophthalmologist according to current standards of care. Patients with diabetes who report any visual symptoms should be promptly referred to an ophthalmologist, regardless of the patient's underlying medications or other physical findings [see Adverse Reactions (6.1)].

5.11 Macrovascular Outcomes

There have been no clinical studies establishing conclusive evidence of macrovascular risk reduction with DUETACT.

6 ADVERSE REACTIONS

The following serious adverse reactions are discussed elsewhere in the labeling:

- Congestive Heart Failure [see Boxed Warning and Warnings and Precautions (5.1)]
- Hypoglycemia [see Warnings and Precautions (5.2)]
- Edema [see Warnings and Precautions (5.7)]
- Fractures [see Warnings and Precautions (5.8)]
- Hemolytic Anemia [see Warnings and Precautions (5.9)]

6.1 Clinical Trials Experience

Because clinical trials are conducted under widely varying conditions, adverse reaction rates observed in the clinical trials of a drug cannot be directly compared to rates in the clinical trials of another drug and may not reflect the rates observed in practice.

The adverse events reported in at least 5% of patients in the controlled 16-week clinical studies between placebo plus a sulfonylurea and pioglitazone (15 mg and 30 mg combined) plus sulfonylurea treatment arms were upper respiratory tract infection (15.5% and 16.6%), accidental injury (8.6% and 3.5%), and combined edema/peripheral edema (2.1% and 7.2%), respectively.

The incidence and type of adverse events reported in at least 5% of patients in any combined treatment group from the 24-week study comparing pioglitazone 30 mg plus a sulfonylurea and pioglitazone 45 mg plus a sulfonylurea are shown in Table 1; the rate of adverse events resulting in study discontinuation between the two treatment groups was 6% and 9.7%, respectively.

Table 1. Adverse Events that Occurred in ≥5% of Patients in Any Treatment Group During the 24-Week Study
Adverse Event | Pioglitazone 30 mg + Sulfonylurea N=351 n (%) | Pioglitazone 45 mg + Sulfonylurea N=351 n (%)
Hypoglycemia | 47 (13.4) | 55 (15.7)
Upper Respiratory Tract Infection | 43 (12.3) | 52 (14.8)
Weight Increased | 32 (9.1) | 47 (13.4)
Edema Lower Limb | 20 (5.7) | 43 (12.3)
Headache | 25 (7.1) | 14 (4.0)
Urinary Tract Infection | 20 (5.7) | 24 (6.8)
Diarrhea | 21 (6.0) | 15 (4.3)
Nausea | 18 (5.1) | 14 (4.0)
Pain in Limb | 19 (5.4) | 14 (4.0)

In US double-blind studies, anemia was reported in ≤2% of patients treated with pioglitazone plus a sulfonylurea [see Warnings and Precautions (5.9)].

Pioglitazone

Over 8500 patients with type 2 diabetes have been treated with pioglitazone in randomized, double-blind, controlled clinical trials, including 2605 patients with type 2 diabetes and macrovascular disease treated with pioglitazone in the PROactive clinical trial. In these trials, over 6000 patients have been treated with pioglitazone for six months or longer, over 4500 patients have been treated with pioglitazone for one year or longer, and over 3000 patients have been treated with pioglitazone for at least two years.

In six pooled 16- to 26-week placebo-controlled monotherapy and 16- to 24-week add-on combination therapy trials, the incidence of withdrawals due to adverse events was 4.5% for patients treated with pioglitazone and 5.8% for comparator-treated patients. The most common adverse events leading to withdrawal were related to inadequate glycemic control, although the incidence of these events was lower (1.5%) with pioglitazone than with placebo (3.0%).

In the PROactive trial, the incidence of withdrawals due to adverse events was 9.0% for patients treated with pioglitazone and 7.7% for placebo-treated patients. Congestive heart failure was the most common serious adverse event leading to withdrawal occurring in 1.3% of patients treated with pioglitazone and 0.6% of patients treated with placebo.

Common Adverse Events: 16- to 26-Week Monotherapy Trials:

A summary of the incidence and type of common adverse events reported in three pooled 16- to 26-week placebo-controlled monotherapy trials of pioglitazone is provided in Table 2. Terms that are reported represent those that occurred at an incidence of >5% and more commonly in patients treated with pioglitazone than in patients who received placebo. None of these adverse events were related to the pioglitazone dose.

Table 2. Three Pooled 16- to 26-Week Placebo-Controlled Clinical Trials of Pioglitazone Monotherapy: Adverse Events Reported at an Incidence >5% and More Commonly in Patients Treated with Pioglitazone than in Patients Treated with Placebo
% of Patients
 | Placebo N=259 | Pioglitazone N=606
Upper Respiratory Tract Infection | 8.5 | 13.2
Headache | 6.9 | 9.1
Sinusitis | 4.6 | 6.3
Myalgia | 2.7 | 5.4
Pharyngitis | 0.8 | 5.1

A summary of the overall incidence and types of common adverse events reported in the PROactive trial is provided in Table 3. Terms that are reported represent those that occurred at an incidence of >5% and more commonly in patients treated with pioglitazone than in patients who received placebo.

Table 3. PROactive Trial: Incidence and Types of Adverse Events Reported in >5% of Patients Treated with Pioglitazone and More Commonly than Placebo
 | % of Patients
 | Placebo N=2633 | Pioglitazone N=2605
Hypoglycemia | 18.8 | 27.3
Edema | 15.3 | 26.7
Cardiac Failure | 6.1 | 8.1
Pain in Extremity | 5.7 | 6.4
Back Pain | 5.1 | 5.5
Chest Pain | 5.0 | 5.1
Mean duration of patient follow-up was 34.5 months.

Congestive Heart Failure

A summary of the incidence of adverse events related to congestive heart failure is provided in Table 4 for the 16- to 24-week add-on to sulfonylurea trials, for the 16- to 24-week add-on to insulin trials, and for the 16- to 24-week add-on to metformin trials. None of the events were fatal.

Table 4. Treatment-Emergent Adverse Events of Congestive Heart Failure (CHF)
Patients Treated with Pioglitazone or Placebo Added on to a Sulfonylurea
 | Number (%) of Patients
 | Placebo-Controlled Trial (16 weeks) |  |  | Non-Controlled Double Blind Trial (24 weeks)
 | Placebo + Sulfonylurea N=187 | Pioglitazone 15 mg + Sulfonylurea N=184 | Pioglitazone 30 mg + Sulfonylurea N=189 | Pioglitazone 30 mg + Sulfonylurea N=351 | Pioglitazone 45 mg + Sulfonylurea N=351
At least one congestive heart failure event | 2 (1.1%) | 0 | 0 | 1 (0.3%) | 6 (1.7%)
Hospitalized | 2 (1.1%) | 0 | 0 | 0 | 2 (0.6%)
Patients Treated with Pioglitazone or Placebo Added on to Insulin
 | Number (%) of Patients
 | Placebo-Controlled Trial (16 weeks) |  |  | Non-Controlled Double Blind Trial (24 weeks)
 | Placebo + Insulin N=187 | Pioglitazone 15 mg + Insulin N=191 | Pioglitazone 30 mg + Insulin N=188 | Pioglitazone 30 mg + Insulin N=345 | Pioglitazone 45 mg + Insulin N=345
At least one congestive heart failure event | 0 | 2 (1.0%) | 2 (1.1%) | 3 (0.9%) | 5 (1.4%)
Hospitalized | 0 | 2 (1.0%) | 1 (0.5%) | 1 (0.3%) | 3 (0.9%)
Patients Treated with Pioglitazone or Placebo Added on to Metformin
 | Number (%) of Patients
 | Placebo-Controlled Trial (16 weeks) |  |  | Non-Controlled Double Blind Trial (24 weeks)
 | Placebo + Metformin N=160 | Pioglitazone 30 mg + Metformin N=168 |  | Pioglitazone 30 mg + Metformin N=411 | Pioglitazone 45 mg + Metformin N=416
At least one congestive heart failure event | 0 | 1 (0.6%) |  | 0 | 1 (0.2%)
Hospitalized | 0 | 1 (0.6%) |  | 0 | 1 (0.2%)

Patients with type 2 diabetes and NYHA class II or early class III congestive heart failure were randomized to receive 24 weeks of double-blind treatment with either pioglitazone at daily doses of 30 mg to 45 mg (n=262) or glyburide at daily doses of 10 mg to 15 mg (n=256). A summary of the incidence of adverse events related to congestive heart failure reported in this study is provided in Table 5.

Table 5. Treatment-Emergent Adverse Events of Congestive Heart Failure (CHF) in Patients with NYHA Class II or III Congestive Heart Failure Treated with Pioglitazone or Glyburide
 | Number (%) of Subjects
 | Pioglitazone N=262 | Glyburide N=256
Death due to cardiovascular causes (adjudicated) | 5 (1.9%) | 6 (2.3%)
Overnight hospitalization for worsening CHF (adjudicated) | 26 (9.9%) | 12 (4.7%)
Emergency room visit for CHF (adjudicated) | 4 (1.5%) | 3 (1.2%)
Patients experiencing CHF progression during study | 35 (13.4%) | 21 (8.2%)

Congestive heart failure events leading to hospitalization that occurred during the PROactive trial are summarized in Table 6.

Table 6. Treatment-Emergent Adverse Events of Congestive Heart Failure (CHF) in PROactiveTrial
 | Number (%) of Patients
 | Placebo N=2633 | Pioglitazone N=2605
At least one hospitalized CHF event | 108 (4.1%) | 149 (5.7%)
Fatal | 22 (0.8%) | 25 (1%)
Hospitalized, nonfatal | 86 (3.3%) | 124 (4.7%)

Cardiovascular Safety

In the PROactive trial, 5238 patients with type 2 diabetes and a history of macrovascular disease were randomized to pioglitazone (N=2605), force-titrated up to 45 mg daily or placebo (N=2633) in addition to standard of care. Almost all patients (95%) were receiving cardiovascular medications (beta blockers, ACE inhibitors, angiotensin II receptor blockers, calcium channel blockers, nitrates, diuretics, aspirin, statins, and fibrates). At baseline, patients had a mean age of 62 years, mean duration of diabetes of 9.5 years, and mean HbA1c of 8.1%. Mean duration of follow-up was 34.5 months.

The primary objective of this trial was to examine the effect of pioglitazone on mortality and macrovascular morbidity in patients with type 2 diabetes mellitus who were at high risk for macrovascular events. The primary efficacy variable was the time to the first occurrence of any event in a cardiovascular composite endpoint that included all-cause mortality, nonfatal myocardial infarction (MI) including silent MI, stroke, acute coronary syndrome, cardiac intervention including coronary artery bypass grafting or percutaneous intervention, major leg amputation above the ankle, and bypass surgery or revascularization in the leg. A total of 514 (19.7%) patients treated with pioglitazone and 572 (21.7%) placebo-treated patients experienced at least one event from the primary composite endpoint (hazard ratio 0.90; 95% Confidence Interval: 0.80, 1.02; p=0.10).

Although there was no statistically significant difference between pioglitazone and placebo for the three-year incidence of a first event within this composite, there was no increase in mortality or in total macrovascular events with pioglitazone. The number of first occurrences and total individual events contributing to the primary composite endpoint is shown in Table 7.

Table 7. PROactive: Number of First and Total Events for Each Component within the Cardiovascular Composite Endpoint
Cardiovascular Events | Placebo N=2633 |  | Pioglitazone N=2605
Cardiovascular Events | First Events n (%) | Total Events n | First Events n (%) | Total Events n
Any event | 572 (21.7) | 900 | 514 (19.7) | 803
All-cause mortality | 122 (4.6) | 186 | 110 (4.2) | 177
Non-fatal myocardial infarction (MI) | 118 (4.5) | 157 | 105 (4.0) | 131
Stroke | 96 (3.6) | 119 | 76 (2.9) | 92
Acute coronary syndrome | 63 (2.4) | 78 | 42 (1.6) | 65
Cardiac intervention (CABG/PCI) | 101 (3.8) | 240 | 101 (3.9) | 195
Major leg amputation | 15 (0.6) | 28 | 9 (0.3) | 28
Leg revascularization | 57 (2.2) | 92 | 71 (2.7) | 115
CABG = coronary artery bypass grafting; PCI = percutaneous intervention

Weight Gain

Dose-related weight gain occurs when pioglitazone is used alone or in combination with other antidiabetic medications. The mechanism of weight gain is unclear but probably involves a combination of fluid retention and fat accumulation.

Tables 8 and 9 summarize the changes in body weight with pioglitazone and placebo in the 16- to 26-week randomized, double-blind monotherapy and 16- to 24-week combination add-on therapy trials and in the PROactive trial.

Table 8. Weight Changes (kg) from Baseline during Randomized, Double-Blind Clinical Trials
 |  | Control Group (Placebo) | Pioglitazone 15 mg | Pioglitazone 30 mg | Pioglitazone 45 mg
 |  | Median (25th/75th percentile) | Median (25th/75th percentile) | Median (25th/75th percentile) | Median (25th/75th percentile)
Monotherapy (16 to 26 weeks) |  | -1.4 (-2.7/0.0) N=256 | 0.9 (-0.5/3.4) N=79 | 1.0 (-0.9/3.4) N=188 | 2.6 (0.2/5.4) N=79
Combination Therapy (16 to 24 weeks) | Sulfonylurea | -0.5 (-1.8/0.7) N=187 | 2.0 (0.2/3.2) N=183 | 3.1 (1.1/5.4) N=528 | 4.1 (1.8/7.3) N=333
Combination Therapy (16 to 24 weeks) | Metformin | -1.4 (-3.2/0.3) N=160 | N/A | 0.9 (-1.3/3.2) N=567 | 1.8 (-0.9/5.0) N=407
Combination Therapy (16 to 24 weeks) | Insulin | 0.2 (-1.4/1.4) N=182 | 2.3 (0.5/4.3) N=190 | 3.3 (0.9/6.3) N=522 | 4.1 (1.4/6.8) N=338

Table 9. Median Change in Body Weight in Patients Treated with Pioglitazone vs Patients Treated with Placebo During the Double-Blind Treatment Period in the PROactive Trial
 | Placebo | Pioglitazone
 | Median (25th/75th percentile) | Median (25th/75th percentile)
Change from baseline to final visit (kg) | -0.5 (-3.3, 2.0) N=2581 | +3.6 (0.0, 7.5) N=2560
Note: Median exposure for both Pioglitazone and Placebo was 2.7 years

Edema

Edema induced from taking pioglitazone is reversible when pioglitazone is discontinued. The edema usually does not require hospitalization unless there is coexisting congestive heart failure. A summary of the frequency and types of edema adverse events occurring in clinical investigations of pioglitazone is provided in Table 10.

Table 10. Adverse Events of Edema in Patients Treated with Pioglitazone
 |  | Number (%) of Patients
 |  | Placebo | Pioglitazone 15 mg | Pioglitazone 30 mg | Pioglitazone 45 mg
Monotherapy (16 to 26 weeks) |  | 3 (1.2%) N=259 | 2 (2.5%) N= 81 | 13 (4.7%) N= 275 | 11 (6.5%) N=169
Combined Therapy (16 to 24 weeks) | Sulfonylurea | 4 (2.1%) N=187 | 3 (1.6%) N=184 | 61 (11.3%) N=540 | 81 (23.1%) N=351
Combined Therapy (16 to 24 weeks) | Metformin | 4 (2.5%) N=160 | N/A | 34 (5.9%) N=579 | 58 (13.9%) N=416
Combined Therapy (16 to 24 weeks) | Insulin | 13 (7.0%) N=187 | 24 (12.6%) N=191 | 109 (20.5%) N=533 | 90 (26.1%) N=345
Note: The preferred terms of edema peripheral, generalized edema, pitting edema and fluid retention were combined to form the aggregate term of "edema."

Table 11. Adverse Events of Edema in Patients in the PROactive Trial
Number (%) of Patients
Placebo N=2633 | Pioglitazone N=2605
419 (15.9%) | 712 (27.3%)
Note: The preferred terms of edema peripheral, generalized edema, pitting edema and fluid retention were combined to form the aggregate term of "edema."

Hepatic Effects

There has been no evidence of pioglitazone-induced hepatotoxicity in the pioglitazone-controlled clinical trial database to date. One randomized, double-blind, 3-year trial comparing pioglitazone to glyburide as add-on to metformin and insulin therapy was specifically designed to evaluate the incidence of serum ALT elevation to greater than three times the upper limit of the reference range, measured every eight weeks for the first 48 weeks of the trial then every 12 weeks thereafter. A total of 3/1051 (0.3%) patients treated with pioglitazone and 9/1046 (0.9%) patients treated with glyburide developed ALT values greater than three times the upper limit of the reference range. None of the patients treated with pioglitazone in the pioglitazone-controlled clinical trial database to date have had a serum ALT greater than three times the upper limit of the reference range and a corresponding total bilirubin greater than two times the upper limit of the reference range, a combination predictive of the potential for severe drug-induced liver injury.

Hypoglycemia

In the pioglitazone clinical trials, adverse events of hypoglycemia were reported based on clinical judgment of the investigators and did not require confirmation with fingerstick glucose testing.

In the 16-week add-on to sulfonylurea trial, the incidence of reported hypoglycemia was 3.7% with pioglitazone 30 mg and 0.5% with placebo. In the 16-week add-on to insulin trial, the incidence of reported hypoglycemia was 7.9% with pioglitazone 15 mg, 15.4% with pioglitazone 30 mg, and 4.8% with placebo.

The incidence of reported hypoglycemia was higher with pioglitazone 45 mg compared to pioglitazone 30 mg in both the 24-week add-on to sulfonylurea trial (15.7% versus 13.4%) and in the 24-week add-on to insulin trial (47.8% versus 43.5%).

Three patients in these four trials were hospitalized due to hypoglycemia. All three patients were receiving pioglitazone 30 mg (0.9%) in the 24-week add-on to insulin trial. An additional 14 patients reported severe hypoglycemia (defined as causing considerable interference with patient's usual activities) that did not require hospitalization. These patients were receiving pioglitazone 45 mg in combination with sulfonylurea (N=2) or pioglitazone 30 mg or 45 mg in combination with insulin (N=12).

Urinary Bladder Tumors

Tumors were observed in the urinary bladder of male rats in the two-year carcinogenicity study [see Nonclinical Toxicology (13.1)]. During the three year PROactive clinical trial, 14 patients out of 2605 (0.54%) randomized to pioglitazone and 5 out of 2633 (0.19%) randomized to placebo were diagnosed with bladder cancer. After excluding patients in whom exposure to study drug was less than one year at the time of diagnosis of bladder cancer, there were 6 (0.23%) cases on pioglitazone and two (0.08%) cases on placebo. After completion of the trial, a large subset of patients was observed for up to 10 additional years, with little additional exposure to pioglitazone. During the 13 years of both PROactive and observational follow-up, the occurrence of bladder cancer did not differ between patients randomized to pioglitazone or placebo (HR =1.00; 95% CI: 0.59-1.72) [see Warnings and Precautions (5.6)].

Glimepiride

Adverse events that occurred in controlled clinical trials with placebo and glimepiride monotherapy, other than hypoglycemia, included: headache (7.8% and 8.2%), accidental injury (3.4% and 5.8%), flu syndrome (4.4% and 5.4%), nausea (3.4% and 5.0%) and dizziness (2.4% and 5.0%), respectively.

Hypoglycemia

In a randomized, double-blind, placebo-controlled monotherapy trial of 14 weeks duration, patients already on sulfonylurea therapy underwent a 3-week washout period then were randomized to glimepiride 1 mg, 4 mg, 8 mg or placebo. Patients randomized to glimepiride 4 mg or 8 mg underwent forced-titration from an initial dose of 1 mg to these final doses, as tolerated. The overall incidence of possible hypoglycemia (defined by the presence of at least one symptom that the investigator believed might be related to hypoglycemia; a concurrent glucose measurement was not required) was 4% for glimepiride 1 mg, 17% for glimepiride 4 mg, 16% for glimepiride 8 mg and 0% for placebo. All of these events were self-treated.

In a randomized, double-blind, placebo-controlled monotherapy trial of 22 weeks duration, patients received a starting dose of either 1 mg glimepiride or placebo daily. The dose of glimepiride was titrated to a target fasting plasma glucose of 90 −150 mg/dL. Final daily doses of glimepiride were 1, 2, 3, 4, 6 or 8 mg. The overall incidence of possible hypoglycemia (as defined above for the 14-week trial) for glimepiride versus placebo was 19.7% vs. 3.2%. All of these events were self-treated.

Weight Gain

Glimepiride, like all sulfonylureas, can cause weight gain.

Allergic Reactions

In clinical trials, allergic reactions, such as pruritus, erythema, urticaria, and morbilliform or maculopapular eruptions, occurred in less than 1% of glimepiride-treated patients. These may resolve despite continued treatment with glimepiride. There are postmarketing reports of more serious allergic reactions (e.g., dyspnea, hypotension, shock) [see Warnings and Precautions (5.3)].

Laboratory Tests

Elevated Serum Alanine Aminotransferase (ALT)

In 11 pooled placebo-controlled trials of glimepiride, 1.9% of glimepiride-treated patients and 0.8% of placebo-treated patients developed serum ALT greater than two times the upper limit of the reference range.

Laboratory Abnormalities

Pioglitazone

Hematologic Effects

Pioglitazone may cause decreases in hemoglobin and hematocrit. In placebo-controlled monotherapy trials, mean hemoglobin values declined by 2% to 4% in patients treated with pioglitazone compared with a mean change in hemoglobin of -1% to +1% in placebo-treated patients. These changes primarily occurred within the first 4 to 12 weeks of therapy and remained relatively constant thereafter. These changes may be related to increased plasma volume associated with pioglitazone therapy and are not likely to be associated with any clinically significant hematologic effects.

Creatine Phosphokinase

During protocol-specified measurement of serum creatine phosphokinase (CPK) in pioglitazone clinical trials, an isolated elevation in CPK to greater than 10 times the upper limit of the reference range was noted in nine (0.2%) patients treated with pioglitazone (values of 2150 to 11400 IU/L) and in no comparator-treated patients. Six of these nine patients continued to receive pioglitazone, two patients were noted to have the CPK elevation on the last day of dosing and one patient discontinued pioglitazone due to the elevation. These elevations resolved without any apparent clinical sequelae. The relationship of these events to pioglitazone therapy is unknown.

6.2 Postmarketing Experience

The following adverse reactions have been identified during post-approval use of pioglitazone and glimepiride. Because these reactions are reported voluntarily from a population of uncertain size, it is generally not possible to reliably estimate their frequency or establish a causal relationship to drug exposure.

Pioglitazone

- New onset or worsening diabetic macular edema with decreased visual acuity [see Warnings and Precautions (5.10)].
- Fatal and nonfatal hepatic failure [see Warnings and Precautions (5.5)].

Postmarketing reports of congestive heart failure have been reported in patients treated with pioglitazone, both with and without previously known heart disease and both with and without concomitant insulin administration.

In postmarketing experience, there have been reports of unusually rapid increases in weight and increases in excess of that generally observed in clinical trials. Patients who experience such increases should be assessed for fluid accumulation and volume-related events such as excessive edema and congestive heart failure [see Boxed Warning and Warnings and Precautions (5.1)].

Glimepiride

- Serious hypersensitivity reactions, including anaphylaxis, angioedema, and Stevens-Johnson Syndrome [see Warnings and Precautions (5.3)]
- Hemolytic anemia in patients with and without G6PD deficiency [see Warnings and Precautions (5.9)]
- Impairment of liver function (e.g. with cholestasis and jaundice), as well as hepatitis, which may progress to liver failure.
- Porphyria cutanea tarda, photosensitivity reactions and allergic vasculitis
- Leukopenia, agranulocytosis, aplastic anemia, and pancytopenia
- Thrombocytopenia (including severe cases with platelet count less than 10,000/mcL) and thrombocytopenic purpura
- Hepatic porphyria reactions and disulfiram-like reactions
- Hyponatremia and syndrome of inappropriate antidiuretic hormone secretion (SIADH), most often in patients who are on other medications or who have medical conditions known to cause hyponatremia or increase release of antidiuretic hormone

7 DRUG INTERACTIONS

7.1 Strong CYP2C8 Inhibitors

Pioglitazone

An inhibitor of CYP2C8 (e.g., gemfibrozil) significantly increases the exposure (area under the serum concentration-time curve or AUC) and half-life (t½) of pioglitazone. Therefore, the maximum recommended dose of pioglitazone is 15 mg daily if used in combination with gemfibrozil or other strong CYP2C8 inhibitors. Since the minimum dose of pioglitazone in DUETACT exceeds 15 mg, patients taking concomitant strong CYP2C8 inhibitors should switch to individual components of DUETACT, unless the prescribing health care provider determines that the benefit of DUETACT clearly outweighs the risk of increased pioglitazone exposure [see Dosage and Administration (2.3) and Clinical Pharmacology (12.3)].

7.2 CYP2C8 Inducers

Pioglitazone

An inducer of CYP2C8 (e.g., rifampin) may significantly decrease the exposure (AUC) of pioglitazone. Therefore, if an inducer of CYP2C8 is started or stopped during treatment with pioglitazone, changes in diabetes treatment may be needed based on clinical response without exceeding the maximum recommended daily dose of 45 mg for pioglitazone [see Clinical Pharmacology (12.3)].

7.3 Topiramate

Pioglitazone

A decrease in the exposure of pioglitazone and its active metabolites were noted with concomitant administration of pioglitazone and topiramate [see Clinical Pharmacology (12.3)]. The clinical relevance of this decrease is unknown; however, when DUETACT and topiramate are used concomitantly, monitor patients for adequate glycemic control.

7.4 Drugs Affecting Glucose Metabolism

Glimepiride

A number of medications affect glucose metabolism and may require DUETACT dose adjustment and particularly close monitoring for hypoglycemia or worsening glycemic control.

The following are examples of medications that may increase the glucose-lowering effect of sulfonylureas including glimepiride, a component of DUETACT, increasing the susceptibility to and/or intensity of hypoglycemia: oral anti-diabetic medications, pramlintide acetate, insulin, angiotensin converting enzyme (ACE) inhibitors, H2 receptor antagonists, fibrates, propoxyphene, pentoxifylline, somatostatin analogs, anabolic steroids and androgens, cyclophosphamide, phenyramidol, guanethidine, fluconazole, sulfinpyrazone, tetracyclines, clarithromycin, disopyramide, quinolones, and those drugs that are highly protein-bound, such as fluoxetine, nonsteroidal anti-inflammatory drugs, salicylates, sulfonamides, chloramphenicol, coumarins, probenecid and monoamine oxidase inhibitors. When these medications are administered to a patient receiving DUETACT, monitor the patient closely for hypoglycemia. When these medications are withdrawn from a patient receiving DUETACT, monitor the patient closely for worsening glycemic control.

The following are examples of medications that may reduce the glucose-lowering effect of sulfonylureas including glimepiride, leading to worsening glycemic control: danazol, glucagon, somatropin, protease inhibitors, atypical antipsychotic medications (e.g., olanzapine and clozapine), barbiturates, diazoxide, laxatives, rifampin, thiazides and other diuretics, corticosteroids, phenothiazines, thyroid hormones, estrogens, oral contraceptives, phenytoin, nicotinic acid, sympathomimetics (e.g., epinephrine, albuterol, terbutaline), and isoniazid. When these medications are administered to a patient receiving DUETACT, monitor the patient closely for worsening glycemic control. When these medications are withdrawn from a patient receiving DUETACT, monitor the patient closely for hypoglycemia.

Beta-blockers, clonidine, and reserpine may lead to either potentiation or weakening of DUETACT's glucose-lowering effect.

Both acute and chronic alcohol intake may potentiate or weaken the glucose-lowering action of DUETACT in an unpredictable fashion.

The signs of hypoglycemia may be reduced or absent in patients taking sympatholytic drugs such as beta-blockers, clonidine, guanethidine, and reserpine.

7.5 Miconazole

Glimepiride

A potential interaction between oral miconazole and sulfonylureas leading to severe hypoglycemia has been reported. Whether this interaction also occurs with other dosage forms of miconazole is not known.

7.6 CYP2C9 Interactions

Glimepiride

There may be an interaction between glimepiride and inhibitors (e.g., fluconazole) and inducers (e.g., rifampin) of CYP2C9. Fluconazole may inhibit the metabolism of glimepiride, causing increased plasma concentrations of glimepiride which may lead to hypoglycemia. Rifampin may induce the metabolism of glimepiride, causing decreased plasma concentrations of glimepiride which may lead to worsening glycemic control.

7.7 Concomitant Administration of Colesevelam

Glimepiride

Colesevelam can reduce the maximum plasma concentrations and total exposure of glimepiride when the two are coadministered. However, absorption is not reduced when glimepiride is administered four hours prior to colesevelam. Therefore, DUETACT should be administered at least four hours prior to colesevelam [see Clinical Pharmacology (12.3)].

8 USE IN SPECIFIC POPULATIONS

8.1 Pregnancy

Risk Summary

Limited data with DUETACT or pioglitazone in pregnant women are not sufficient to determine a drug-associated risk for major birth defects or miscarriage. There are clinical considerations related to fetal and neonatal adverse reactions and drug discontinuation if glimepiride is used during pregnancy. There are risks to the mother and fetus associated with poorly controlled diabetes in pregnancy [see Clinical Considerations].

No adverse developmental effects were observed when pioglitazone was administered to pregnant rats and rabbits during organogenesis at exposures up to 5- and 35- times the 45 mg clinical dose, respectively, based on the body surface area. Administration of glimepiride to pregnant rats and rabbits during organogenesis induced maternal hypoglycemia and also increased fetal mortality at doses 50 (rats) and 0.1-times (rabbits) the 8 mg clinical dose, respectively, based on body surface area [see Data].

The estimated background risk of major birth defects is 6-10% in women with pre-gestational diabetes with a HbA1c >7 and has been reported to be as high as 20-25% in women with a HbA1c >10. The estimated background risk of miscarriage for the indicated population is unknown. In the U.S. general population, the estimated background risk of major birth defects and miscarriage in clinically recognized pregnancies is 2-4% and 15-20% respectively.

Clinical Considerations

Disease-associated maternal and/or embryo/fetal risk

Poorly controlled diabetes in pregnancy increases the maternal risk for diabetic ketoacidosis, pre-eclampsia, spontaneous abortions, preterm delivery, still birth and delivery complications. Poorly controlled diabetes increases the fetal risk for major birth defects, still birth, and macrosomia related morbidity.

Fetal/Neonatal Adverse Reaction

Neonates of women with gestational diabetes, who are treated with sulfonylureas during pregnancy, may be at increased risk for neonatal intensive care unit admission, and may develop respiratory distress, hypoglycemia, birth injury, and be large for gestational age. Prolonged severe hypoglycemia, lasting 4-10 days, has been reported in neonates born to mothers receiving a sulfonylurea at the time of delivery and has been reported with the use of agents with a prolonged half-life. Observe newborns for symptoms of hypoglycemia and respiratory distress and manage accordingly.

Dose adjustments during pregnancy and the postpartum period

Due to reports of prolonged severe hypoglycemia in neonates born to mothers receiving a sulfonylurea at the time of delivery, DUETACT should be discontinued at least two weeks before expected delivery [see Fetal/Neonatal Adverse Reaction].

Data

Animal Data

Pioglitazone and Glimepiride

Animal reproduction studies were not conducted with the combined products in DUETACT. The following data are based on studies conducted with the individual components of DUETACT.

Pioglitazone

Pioglitazone administered to pregnant rats during organogenesis did not cause adverse developmental effects at a dose of 20 mg/kg (~5-times the 45 mg clinical dose), but delayed parturition and reduced embryofetal viability at 40 and 80 mg/kg, or ≥9-times the 45 mg clinical dose, by body surface area. In pregnant rabbits administered pioglitazone during organogenesis, no adverse developmental effects were observed at 80 mg/kg (~35-times the 45 mg clinical dose), but reduced embryofetal viability at 160 mg/kg, or ~69-times the 45 mg clinical dose, by body surface area. When pregnant rats received pioglitazone during late gestation and lactation, delayed postnatal development, attributed to decreased body weight occurred in offspring at maternal doses of 10 mg/kg and above or ≥2 times the 45 mg clinical dose, by body surface area.

Glimepiride

Fetal deaths occurred in rats and rabbits administered glimepiride during the period of organogenesis at doses 50-times (rats) and 0.1-times (rabbits) the 8 mg clinical dose, based on body surface area. This fetotoxicity, observed only at doses inducing maternal hypoglycemia, is believed to be directly related to the pharmacologic (hypoglycemic) action of glimepiride and has been similarly noted with other sulfonylureas.

8.2 Lactation

Risk Summary

There is no information regarding the presence of pioglitazone or glimepiride in human milk, the effects on the breastfed infant, or the effects on milk production. Pioglitazone and glimepiride are present in rat milk; however, due to species-specific differences in lactation physiology, animal data may not reliably predict drug levels in human milk [see Data].

The developmental and health benefits of breastfeeding should be considered along with the mother's clinical need for DUETACT and any potential adverse effects on the breastfed infant from DUETACT or from the underlying maternal condition.

Data

During pre- and postnatal studies in rats, glimepiride was present in lactational milk and in serum of nursing rat pups. Offspring exposed to high levels of glimepiride during lactation developed skeletal abnormalities (shortening, thickening and bending of the humerus) during the postnatal period.

8.3 Females and Males of Reproductive Potential

Discuss the potential for unintended pregnancy with premenopausal women as therapy with pioglitazone, like other thiazolidinediones, may result in ovulation in some anovulatory women.

8.4 Pediatric Use

Safety and effectiveness of DUETACT in pediatric patients have not been established.

DUETACT is not recommended for use in pediatric patients based on adverse effects observed in adults, including fluid retention and congestive heart failure, fractures, and urinary bladder tumors [see Warnings and Precautions (5.1, 5.6, 5.7, 5.8)].

Glimepiride

The pharmacokinetics, efficacy and safety of glimepiride have been evaluated in pediatric patients with type 2 diabetes as described below. Glimepiride is not recommended in pediatric patients because of its adverse effects on body weight and hypoglycemia.

The pharmacokinetics of a 1 mg single dose of glimepiride was evaluated in 30 patients with type 2 diabetes (male = 7; female = 23) between ages 10 and 17 years. The mean (±SD) AUC (0-last) (339±203 ng•hr/mL), Cmax (102±48 ng/mL) and t1/2 (3.1±1.7 hours) for glimepiride were comparable to historical data from adults (AUC (0-last) 315±96 ng•hr/mL, Cmax 103±34 ng/mL and t1/2 5.3±4.1 hours).

The safety and efficacy of glimepiride in pediatric patients was evaluated in a single-blind, 24-week trial that randomized 272 patients (8 to 17 years of age) with type 2 diabetes to glimepiride (n=135) or metformin (n=137). Both treatment-naïve patients (those treated with only diet and exercise for at least two weeks prior to randomization) and previously treated patients (those previously treated or currently treated with other oral antidiabetic medications for at least three months) were eligible to participate. Patients who were receiving oral antidiabetic agents at the time of study entry discontinued these medications before randomization without a washout period. Glimepiride was initiated at 1 mg, and then titrated up to 2, 4 or 8 mg (mean last dose 4 mg) through Week 12, targeting a self monitored fasting fingerstick blood glucose <126 mg/dL. Metformin was initiated at 500 mg twice daily and titrated at Week 12 up to 1000 mg twice daily (mean last dose 1365 mg).

After 24 weeks, the overall mean treatment difference in HbA1c between glimepiride and metformin was 0.2%, favoring metformin (95% confidence interval -0.3% to +0.6%).

Based on these results, the trial did not meet its primary objective of showing a similar reduction in HbA1c with glimepiride compared to metformin.

The profile of adverse reactions in pediatric patients treated with glimepiride was similar to that observed in adults.

Hypoglycemic events documented by blood glucose values <36 mg/dL were observed in 4% of pediatric patients treated with glimepiride and in 1% of pediatric patients treated with metformin. One patient in each treatment group experienced a severe hypoglycemic episode (severity was determined by the investigator based on observed signs and symptoms).

8.5 Geriatric Use

To minimize the risk of hypoglycemia, the initial dosing, dose increments, and maintenance dosage of DUETACT should be conservative. During initiation of DUETACT therapy and any subsequent dose adjustments, geriatric patients should be observed carefully for hypoglycemia.

Pioglitazone

A total of 92 patients (15.2%) treated with pioglitazone in the three pooled 16- to 26-week double-blind, placebo-controlled, monotherapy trials were ≥65 years old and two patients (0.3%) were ≥75 years old. In the two pooled 16- to 24-week add-on to sulfonylurea trials, 201 patients (18.7%) treated with pioglitazone were ≥65 years old and 19 (1.8%) were ≥75 years old. In the two pooled 16- to 24-week add-on to metformin trials, 155 patients (15.5%) treated with pioglitazone were ≥65 years old and 19 (1.9%) were ≥75 years old. In the two pooled 16- to 24-week add-on to insulin trials, 272 patients (25.4%) treated with pioglitazone were ≥65 years old and 22 (2.1%) were ≥75 years old.

In PROactive, 1068 patients (41.0%) treated with pioglitazone were ≥65 years old and 42 (1.6%) were ≥75 years old.

In pharmacokinetic studies with pioglitazone, no significant differences were observed in pharmacokinetic parameters between elderly and younger patients [see Clinical Pharmacology (12.3)].

Although clinical experiences have not identified differences in effectiveness and safety between the elderly (≥65 years) and younger patients, these conclusions are limited by small sample sizes for patients ≥75 years old.

Glimepiride

In clinical trials of glimepiride, 1053 of 3491 patients (30%) were ≥65 years of age. No overall differences in safety or effectiveness were observed between these patients and younger patients, but greater sensitivity of some older individuals cannot be ruled out.

There were no significant differences in glimepiride pharmacokinetics between patients with type 2 diabetes ≤65 years (n=49) and those >65 years (n=42) [see Clinical Pharmacology (12.3)].

Glimepiride is substantially excreted by the kidney. Elderly patients are more likely to have renal impairment. In addition, hypoglycemia may be difficult to recognize in the elderly [see Dosage and Administration (2.1) and Warnings and Precautions (5.2)]. Use caution when initiating DUETACT and increasing the dose of DUETACT in this patient population.

8.6 Renal Impairment

To minimize the risk of hypoglycemia, the initial dosing, dose increments and maintenance dosage of DUETACT should be conservative. During initiation of DUETACT therapy and any subsequent dose adjustments, these patients should be observed carefully for hypoglycemia.

A multiple-dose titration study was conducted in 16 patients with type 2 diabetes and renal impairment using doses ranging from 1 mg to 8 mg daily for three months. Baseline creatinine clearance ranged from 10 to 60 mL/min. The pharmacokinetics of glimepiride were evaluated in the multiple-dose titration study and the results were consistent with those observed in patients enrolled in a single-dose study. In both studies, the relative total clearance of glimepiride increased when kidney function was impaired. Both studies also demonstrated that the elimination of the two major metabolites was reduced in patients with renal impairment [see Clinical Pharmacology (12.3)].

10 OVERDOSAGE

Pioglitazone

During controlled clinical trials, one case of overdose with pioglitazone was reported. A male patient took 120 mg per day for four days, then 180 mg per day for seven days. The patient denied any clinical symptoms during this period.

In the event of overdosage, appropriate supportive treatment should be initiated according to the patient's clinical signs and symptoms.

Glimepiride

An overdosage of glimepiride, as with other sulfonylureas, can produce severe hypoglycemia. Mild episodes of hypoglycemia can be treated with oral glucose. Severe hypoglycemic reactions constitute medical emergencies requiring immediate treatment. Severe hypoglycemia with coma, seizure, or neurological impairment can be treated with glucagon or intravenous glucose. Continued observation and additional carbohydrate intake may be necessary because hypoglycemia may recur after apparent clinical recovery [see Warnings and Precautions (5.2)].

11 DESCRIPTION

DUETACT tablets are a thiazolidinedione and a sulfonylurea combination product that contains two oral antihyperglycemic agents: pioglitazone and glimepiride. The concomitant use of pioglitazone and a sulfonylurea, the class of drugs that includes glimepiride, has been previously approved based on clinical trials in patients with type 2 diabetes inadequately controlled on a sulfonylurea. Additional efficacy and safety information about pioglitazone and glimepiride monotherapies may be found in the prescribing information for each individual drug.

Pioglitazone is an oral antidiabetic medication.

Pioglitazone [(±)-5-[[4-[2-(5-ethyl-2-pyridinyl)ethoxy]phenyl]methyl]-2,4-] thiazolidinedione monohydrochloride contains one asymmetric carbon, and the compound is synthesized and used as the racemic mixture. The two enantiomers of pioglitazone interconvert in vivo. No differences were found in the pharmacologic activity between the two enantiomers. The structural formula is as shown:

Pioglitazone hydrochloride is an odorless, white crystalline powder that has a molecular formula of C19H20N2O3S•HCl and a molecular weight of 392.90 daltons. It is soluble in N,N‑dimethylformamide, slightly soluble in anhydrous ethanol, very slightly soluble in acetone and acetonitrile, practically insoluble in water, and insoluble in ether.

Glimepiride is an oral sulfonylurea chemically identified as 1-[[p-[2-(3-ethyl-4-methyl-2-oxo-3-pyrroline-1-carboxamido)ethyl]phenyl]sulfonyl]-3-(trans-4-methylcyclohexyl)-urea (C24H34N4O5S) with a molecular weight of 490.62. Glimepiride is a white to yellowish-white, crystalline, odorless to practically odorless powder and is practically insoluble in water. The structural formula is:

DUETACT is available as a tablet for oral administration containing 30 mg pioglitazone (as the base) with 2 mg glimepiride (30 mg/2 mg) or 30 mg pioglitazone (as the base) with 4 mg glimepiride (30 mg/4 mg) formulated with the following excipients: croscarmellose sodium NF, lactose monohydrate NF, magnesium stearate NF, hydroxypropyl cellulose NF, polysorbate 80 NF, and microcrystalline cellulose NF.

12 CLINICAL PHARMACOLOGY

12.1 Mechanism of Action

DUETACT combines 2 antihyperglycemic agents with different mechanisms of action to improve glycemic control in patients with type 2 diabetes: pioglitazone, a member of the thiazolidinedione class, and glimepiride, a member of the sulfonylurea class. Thiazolidinediones are insulin-sensitizing agents that act primarily by enhancing peripheral glucose utilization, whereas sulfonylureas are insulin secretagogues that act primarily by stimulating release of insulin from functioning pancreatic beta cells.

Pioglitazone

Pioglitazone is a thiazolidinedione that depends on the presence of insulin for its mechanism of action. Pioglitazone decreases insulin resistance in the periphery and in the liver resulting in increased insulin-dependent glucose disposal and decreased hepatic glucose output. Pioglitazone is not an insulin secretagogue. Pioglitazone is an agonist for peroxisome proliferator-activated receptor-gamma (PPARγ). PPAR receptors are found in tissues important for insulin action such as adipose tissue, skeletal muscle, and liver. Activation of PPARγ nuclear receptors modulates the transcription of a number of insulin responsive genes involved in the control of glucose and lipid metabolism.

In animal models of diabetes, pioglitazone reduces the hyperglycemia, hyperinsulinemia, and hypertriglyceridemia characteristic of insulin-resistant states such as type 2 diabetes. The metabolic changes produced by pioglitazone result in increased responsiveness of insulin-dependent tissues and are observed in numerous animal models of insulin resistance.

Because pioglitazone enhances the effects of circulating insulin (by decreasing insulin resistance), it does not lower blood glucose in animal models that lack endogenous insulin.

Glimepiride

Glimepiride primarily lowers blood glucose by stimulating the release of insulin from pancreatic beta cells. Sulfonylureas bind to the sulfonylurea receptor in the pancreatic beta cell plasma membrane, leading to closure of the ATP-sensitive potassium channel, thereby stimulating the release of insulin.

12.2 Pharmacodynamics

Pioglitazone

Clinical studies demonstrate that pioglitazone improves insulin sensitivity in insulin-resistant patients. Pioglitazone enhances cellular responsiveness to insulin, increases insulin-dependent glucose disposal and improves hepatic sensitivity to insulin. In patients with type 2 diabetes, the decreased insulin resistance produced by pioglitazone results in lower plasma glucose concentrations, lower plasma insulin concentrations, and lower HbA1c values. In controlled clinical trials, pioglitazone had an additive effect on glycemic control when used in combination with a sulfonylurea, metformin, or insulin [see Clinical Studies (14)].

Patients with lipid abnormalities were included in clinical trials with pioglitazone. Overall, patients treated with pioglitazone had mean decreases in serum triglycerides, mean increases in HDL cholesterol, and no consistent mean changes in LDL and total cholesterol. There is no conclusive evidence of macrovascular benefit with pioglitazone [see Warnings and Precautions (5.11) and Adverse Reactions (6.1)].

In a 26-week, placebo-controlled, dose-ranging monotherapy study, mean serum triglycerides decreased in the 15 mg, 30 mg, and 45 mg pioglitazone dose groups compared to a mean increase in the placebo group. Mean HDL cholesterol increased to a greater extent in patients treated with pioglitazone than in the placebo-treated patients. There were no consistent differences for LDL and total cholesterol in patients treated with pioglitazone compared to placebo (Table 12).

Table 12. Lipids in a 26-Week Placebo-Controlled Monotherapy Dose-Ranging Study
 | Placebo | Pioglitazone 15 mg Once Daily | Pioglitazone 30 mg Once Daily | Pioglitazone 45 mg Once Daily
Triglycerides (mg/dL) | N=79 | N=79 | N=84 | N=77
Baseline (mean) | 263 | 284 | 261 | 260
Percent change from baseline (adjusted mean*) | 4.8% | -9.0%† | -9.6%† | -9.3%†
HDL Cholesterol (mg/dL) | N=79 | N=79 | N=83 | N=77
Baseline (mean) | 42 | 40 | 41 | 41
Percent change from baseline (adjusted mean*) | 8.1% | 14.1%† | 12.2% | 19.1%†
LDL Cholesterol (mg/dL) | N=65 | N=63 | N=74 | N=62
Baseline (mean) | 139 | 132 | 136 | 127
Percent change from baseline (adjusted mean*) | 4.8% | 7.2% | 5.2% | 6.0%
Total Cholesterol (mg/dL) | N=79 | N=79 | N=84 | N=77
Baseline (mean) | 225 | 220 | 223 | 214
Percent change from baseline (adjusted mean*) | 4.4% | 4.6% | 3.3% | 6.4%
*Adjusted for baseline, pooled center, and pooled center by treatment interaction
†p <0.05 versus placebo

In the two other monotherapy studies (16 weeks and 24 weeks) and in combination therapy studies with sulfonylurea (16 weeks and 24 weeks), metformin (16 weeks and 24 weeks) or insulin (16 weeks and 24 weeks), the results were generally consistent with the data above.

Glimepiride

In healthy subjects, the time to reach maximal effect (minimum blood glucose concentrations) was approximately by two to three hours after single oral doses of glimepiride. The effects of HbA1C, fasting plasma glucose, and post-prandial glucose have been assessed in clinical trials.

12.3 Pharmacokinetics

Absorption and Bioavailability:

DUETACT

Bioequivalence studies were conducted following a single dose of the DUETACT 30 mg/2 mg and 30 mg/4 mg tablets and concomitant administration of pioglitazone (30 mg) and glimepiride (2 mg or 4 mg) under fasting conditions in healthy subjects.

Based on the area under the curve (AUC) and maximum concentration (Cmax) of both pioglitazone and glimepiride, DUETACT 30 mg/2 mg and 30 mg/4 mg were bioequivalent to pioglitazone 30 mg concomitantly administered with glimepiride (2 mg or 4 mg, respectively).

Food did not change the systemic exposures of glimepiride or pioglitazone following administration of DUETACT. The presence of food did not significantly alter the time to peak serum concentration (Tmax) of glimepiride or pioglitazone and Cmax of pioglitazone. However, for glimepiride, there was a 22% increase in Cmax when DUETACT was administered with food.

Pioglitazone

Following once-daily administration of pioglitazone, steady-state serum concentrations of both pioglitazone and its major active metabolites, M-III (keto derivative of pioglitazone) and M-IV (hydroxyl derivative of pioglitazone), are achieved within seven days. At steady-state, M-III and M-IV reach serum concentrations equal to or greater than that of pioglitazone. At steady-state, in both healthy volunteers and patients with type 2 diabetes, pioglitazone comprises approximately 30% to 50% of the peak total pioglitazone serum concentrations (pioglitazone plus active metabolites) and 20% to 25% of the total AUC.

Cmax, AUC, and trough serum concentrations (Cmin) for pioglitazone and M-III and M-IV, increased proportionally with administered doses of 15 mg and 30 mg per day.

Following oral administration of pioglitazone, Tmax of pioglitazone was within two hours. Food delays Tmax to three to four hours but does not alter the extent of absorption (AUC).

Glimepiride

Studies with single oral doses of glimepiride in healthy subjects and with multiple oral doses in patients with type 2 diabetes showed peak drug concentrations (Cmax) two to three hours post-dose. When glimepiride was given with meals, the mean Cmax and AUC were decreased by 8% and 9%, respectively.

Glimepiride does not accumulate in serum following multiple dosing. The pharmacokinetics of glimepiride does not differ between healthy subjects and patients with type 2 diabetes. Clearance (CL/F) of glimepiride after oral administration does not change over the 1 mg to 8 mg dose range, indicating linear pharmacokinetics.

In healthy subjects, the intra- and inter-individual variabilities of glimepiride pharmacokinetic parameters were 15% to 23% and 24% to 29%, respectively.

Distribution

Pioglitazone

The mean apparent volume of distribution (Vd/F) of pioglitazone following single-dose administration is 0.63 ± 0.41 (mean ± SD) L/kg of body weight. Pioglitazone is extensively protein bound (>99%) in human serum, principally to serum albumin. Pioglitazone also binds to other serum proteins, but with lower affinity. M-III and M-IV are also extensively bound (>98%) to serum albumin.

Glimepiride

After intravenous (IV) dosing in healthy subjects, Vd/F was 8.8 L (113 mL/kg), and the total body clearance (CL) was 47.8 mL/min. Protein binding was greater than 99.5%.

Metabolism

Pioglitazone

Pioglitazone is extensively metabolized by hydroxylation and oxidation; the metabolites also partly convert to glucuronide or sulfate conjugates. Metabolites M-III and M-IV are the major circulating active metabolites in humans.

In vitro data demonstrate that multiple CYP isoforms are involved in the metabolism of pioglitazone which include CYP2C8 and, to a lesser degree, CYP3A4 with additional contributions from a variety of other isoforms including the mainly extrahepatic CYP1A1. In vivo study of pioglitazone in combination with gemfibrozil, a strong CYP2C8 inhibitor, showed that pioglitazone is a CYP2C8 substrate [see Dosage and Administration (2.3) and Drug Interactions (7.1)]. Urinary 6ß-hydroxycortisol/cortisol ratios measured in patients treated with pioglitazone showed that pioglitazone is not a strong CYP3A4 enzyme inducer.

Glimepiride

Glimepiride is completely metabolized by oxidative biotransformation after either an IV or oral dose. The major metabolites are the cyclohexyl hydroxy methyl derivative (M1) and the carboxyl derivative (M2). CYP2C9 is involved in the biotransformation of glimepiride to M1. M1 is further metabolized to M2 by one or several cytosolic enzymes. In animals, M1 possesses about one-third of the pharmacological activity of glimepiride, but it is unclear whether M1 results in clinically meaningful effects on blood glucose in humans. M2 is inactive.

Excretion and Elimination

Pioglitazone

Following oral administration, approximately 15% to 30% of the pioglitazone dose is recovered in the urine. Renal elimination of pioglitazone is negligible and the drug is excreted primarily as metabolites and their conjugates. It is presumed that most of the oral dose is excreted into the bile either unchanged or as metabolites and eliminated in the feces.

The mean serum half-life (t1/2) of pioglitazone and its metabolites (M-III and M-IV) range from three to seven hours and 16 to 24 hours, respectively. Pioglitazone has an apparent clearance, CL/F, calculated to be five to seven L/hr.

Glimepiride

When ^14C-glimepiride was given orally to three healthy male subjects, approximately 60% of the total radioactivity was recovered in the urine in seven days. M1 and M2 accounted for 80% to 90% of the radioactivity recovered in the urine. The ratio of M1 to M2 in the urine was approximately 3:2 in two subjects and 4:1 in one subject. Approximately 40% of the total radioactivity was recovered in feces. M1 and M2 accounted for approximately 70% (ratio of M1 to M2 was 1:3) of the radioactivity recovered in feces. No parent drug was recovered from urine or feces. After IV dosing in patients, no significant biliary excretion of glimepiride or its M1 metabolite was observed.

Renal Impairment

Pioglitazone

The serum elimination half-life of pioglitazone, M-III, and M-IV remains unchanged in patients with moderate [creatinine clearance (CLcr) 30 to 50 mL/min] and severe (CLcr <30 mL/min) renal impairment when compared to subjects with normal renal function. Therefore, no dose adjustment in patients with renal impairment is required.

Glimepiride

In a single-dose, open-label study glimepiride 3 mg was administered to patients with mild, moderate and severe renal impairment as estimated by CLcr: Group I consisted of five patients with mild renal impairment (CLcr >50 mL/min), Group II consisted of 3 patients with moderate renal impairment (CLcr = 20 to 50 mL/min) and Group III consisted of seven patients with severe renal impairment (CLcr <20 mL/min). Although, glimepiride serum concentrations decreased with decreasing renal function, Group III had a 2.3-fold higher mean AUC for M1 and an 8.6-fold higher mean AUC for M2 compared to corresponding mean AUCs in Group I. The t½ for glimepiride did not change, while the t½ for M1 and M2 increased as renal function decreased. Mean urinary excretion of M1 plus M2 as a percentage of dose decreased from 44.4% for Group I to 21.9% for Group II and 9.3% for Group III.

Hepatic Impairment

Pioglitazone

Compared with healthy controls, subjects with impaired hepatic function (Child-Turcotte-Pugh Grade B/C) have an approximate 45% reduction in pioglitazone and total pioglitazone (pioglitazone, M-III, and M-IV) mean Cmax but no change in the mean AUC values. Therefore, no dose adjustment in patients with hepatic impairment is required.

There are postmarketing reports of liver failure with pioglitazone and clinical trials have generally excluded patients with serum ALT >2.5 times the upper limit of the reference range. Use DUETACT with caution in patients with liver disease [see Warnings and Precautions (5.5)].

Glimepiride

It is unknown whether there is an effect of hepatic impairment on glimepiride pharmacokinetics because the pharmacokinetics of glimepiride has not been adequately evaluated in patients with hepatic impairment.

Geriatric Patients

Pioglitazone

In healthy elderly subjects, Cmax of pioglitazone was not significantly different, but AUC values were approximately 21% higher than those achieved in younger subjects. The mean t½ of pioglitazone was also prolonged in elderly subjects (about 10 hours) as compared to younger subjects (about seven hours). These changes were not of a magnitude that would be considered clinically relevant.

Glimepiride

A comparison of glimepiride pharmacokinetics in patients with type 2 diabetes ≤65 years and those >65 years was evaluated in a multiple-dose study using 6 mg daily dose. There were no significant differences in glimepiride pharmacokinetics between the two age groups. The mean AUC at steady state for the older patients was approximately 13% lower than that for the younger patients; the mean weight-adjusted clearance for the older patients was approximately 11% higher than that for the younger patients.

Pediatric Patients

No pharmacokinetic studies of DUETACT were performed in pediatric patients.

Pioglitazone

Safety and efficacy of pioglitazone in pediatric patients have not been established. DUETACT is not recommended for use in pediatric patients [see Use in Specific Populations (8.4)].

Gender

Pioglitazone

The mean Cmax and AUC values of pioglitazone were increased 20% to 60% in women compared to men. In controlled clinical trials, HbA1c decreases from baseline were generally greater for females than for males (average mean difference in HbA1c 0.5%). Because therapy should be individualized for each patient to achieve glycemic control, no dose adjustment is recommended based on gender alone.

Glimepiride

There were no differences between males and females in the pharmacokinetics of glimepiride when adjustment was made for differences in body weight.

Ethnicity

Pioglitazone

Pharmacokinetic data among various ethnic groups are not available.

Glimepiride

No studies have been conducted to assess the effects of race on glimepiride pharmacokinetics but in placebo-controlled trials of glimepiride in patients with type 2 diabetes, the reduction in HbA1c was comparable in Caucasians (n=536), blacks (n=63), and Hispanics (n=63).

Obese Patients

The pharmacokinetics of glimepiride and its metabolites were measured in a single-dose study involving 28 patients with type 2 diabetes who either had normal body weight or were morbidly obese. While the Tmax, CL/F, and Vd/F of glimepiride in the morbidly obese patients were similar to those in the normal weight group, the morbidly obese had lower Cmax and AUC than those of normal body weight. The mean Cmax, AUC0-24, AUC0-∞ values of glimepiride in normal vs. morbidly obese patients were 547 ± 218 ng/mL vs. 410 ± 124 ng/mL, 3210 ± 1030 hours∙ng/mL vs. 2820 ± 1110 hours∙ng/mL and 4000 ± 1320 hours∙ng/mL versus 3280 ± 1360 hours∙ng/mL, respectively.

Drug-Drug Interactions

Coadministration of pioglitazone (45 mg) and a sulfonylurea (5 mg glipizide) administered orally once daily for seven days did not alter the steady-state pharmacokinetics of glipizide. Glimepiride and glipizide have similar metabolic pathways and are mediated by CYP2C9; therefore, drug-drug interaction between pioglitazone and glimepiride is considered unlikely. Specific pharmacokinetic drug interaction studies with DUETACT have not been performed, although such studies have been conducted with the individual pioglitazone and glimepiride components.

Pioglitazone

Table 13. Effect of Pioglitazone Coadministration on Systemic Exposure of Other Drugs
 | Coadministered Drug
Pioglitazone Dosage Regimen (mg)* | Name and Dose Regimens | Change in AUC† |  | Change in Cmax†
45 mg (N=12) | Warfarin‡
45 mg (N=12) | Daily loading then maintenance doses based PT and INR values Quick's Value = 35 ± 5% | R-Warfarin | ↓3% | R-Warfarin | ↓2%
45 mg (N=12) | Daily loading then maintenance doses based PT and INR values Quick's Value = 35 ± 5% | S-Warfarin | ↓1% | S-Warfarin | ↑1%
45 mg (N=12) | Digoxin
45 mg (N=12) | 0.250 mg twice daily (loading dose) then 0.250 mg daily (maintenance dose, 7 days) | ↑15% |  | ↑17%
45 mg daily for 21 days (N=35) | Oral Contraceptive
45 mg daily for 21 days (N=35) | [Ethinyl Estradiol (EE) 0.035 mg plus Norethindrone (NE) 1 mg] for 21 days | EE | ↓11% | EE | ↓13%
45 mg daily for 21 days (N=35) | [Ethinyl Estradiol (EE) 0.035 mg plus Norethindrone (NE) 1 mg] for 21 days | NE | ↑3% | NE | ↓7%
45 mg (N=23) | Fexofenadine
45 mg (N=23) | 60 mg twice daily for 7 days | ↑30% |  | ↑37%
45 mg (N=14) | Glipizide
45 mg (N=14) | 5 mg daily for 7 days | ↓3% |  | ↓8%
45 mg daily for 8 days (N=16) | Metformin
45 mg daily for 8 days (N=16) | 1000 mg single dose on Day 8 | ↓3% |  | ↓5%
45 mg (N=21) | Midazolam
45 mg (N=21) | 7.5 mg single dose on Day 15 | ↓26% |  | ↓26%
45 mg (N=24) | Ranitidine
45 mg (N=24) | 150 mg twice daily for 7 days | ↑1% |  | ↓1%
45 mg daily for 4 days (N=24) | Nifedipine ER
45 mg daily for 4 days (N=24) | 30 mg daily for 4 days | ↓13% |  | ↓17%
45 mg (N=25) | Atorvastatin Ca
45 mg (N=25) | 80 mg daily for 7 days | ↓14% |  | ↓23%
45 mg (N=22) | Theophylline
45 mg (N=22) | 400 mg twice daily for 7 days | ↑2% |  | ↑5%
*Daily for 7 days unless otherwise noted
†% change (with/without coadministered drug and no change = 0%); symbols of ↑ and ↓ indicate the exposure increase and decrease, respectively
‡Pioglitazone had no clinically significant effect on prothrombin time

Table 14. Effect of Coadministered Drugs on Pioglitazone Systemic Exposure
Coadministered Drug and Dosage Regimen | Pioglitazone
Coadministered Drug and Dosage Regimen | Dose Regimen (mg) [Daily for 7 days unless otherwise noted] | Change in AUC [Mean ratio (with/without coadministered drug and no change = 1-fold) % change (with/without coadministered drug and no change = 0%); symbols of ↑ and ↓ indicate the exposure increase and decrease, respectively] | Change in Cmax
Gemfibrozil 600 mg twice daily for 2 days (N=12) | 15 mg single dose | ↑3.2-fold [The half-life of pioglitazone increased from 8.3 hours to 22.7 hours in the presence of gemfibrozil [see Dosage and Administration (2.3) and Drug Interactions (7)]] | ↑6%
Ketoconazole 200 mg twice daily for 7 days (N=28) | 45 mg | ↑34% | ↑14%
Rifampin 600 mg daily for 5 days (N=10) | 30 mg single dose | ↓54% | ↓5%
Fexofenadine 60 mg twice daily for 7 days (N=23) | 45 mg | ↑ 1% | 0%
Ranitidine 150 mg twice daily for 4 days (N=23) | 45 mg | ↓ 13% | ↓16%
Nifedipine ER 30 mg daily for 7 days (N=23) | 45 mg | ↑5% | ↑4%
Atorvastatin Ca 80 mg daily for 7 days (N = 24) | 45 mg | ↓24% | ↓31%
Theophylline 400 mg twice daily for 7 days (N=22) | 45 mg | ↓4% | ↓2%
Topiramate 96 mg twice daily for 7 days [Indicates duration of concomitant administration with highest twice-daily dose of topiramate from Day 14 onwards over the 22 days of study] (N=26) | 30 mg | ↓15% [Additional decrease in active metabolites; 60% for M-III and 16% for M-IV] | 0%

Glimepiride

Aspirin

In a randomized, double-blind, two-period, crossover study, healthy subjects were given either placebo or aspirin 1 gram three times daily for a total treatment period of 5 days. On Day 4 of each study period, a single 1 mg dose of glimepiride was administered. The glimepiride doses were separated by a 14-day washout period. Coadministration of aspirin and glimepiride resulted in a 34% decrease in the mean glimepiride AUC and a 4% decrease in the mean glimepiride Cmax.

Cimetidine and Ranitidine

In a randomized, open-label, 3-way crossover study, healthy subjects received either a single 4 mg dose of glimepiride alone, glimepiride with ranitidine (150 mg twice daily for 4 days; glimepiride was administered on Day 3), or glimepiride with cimetidine (800 mg daily for 4 days; glimepiride was administered on Day 3). Coadministration of cimetidine or ranitidine with a single 4 mg oral dose of glimepiride did not significantly alter the absorption and disposition of glimepiride.

Propranolol

In a randomized, double-blind, two-period, crossover study, healthy subjects were given either placebo or propranolol 40 mg three times daily for a total treatment period of five days. On Day 4 or each study period, a single 2 mg dose of glimepiride was administered. The glimepiride doses were separated by a 14-day washout period. Concomitant administration of propranolol and glimepiride significantly increased glimepiride Cmax, AUC, and t1/2 by 23%, 22%, and 15%, respectively, and decreased glimepiride CL/F by 18%. The recovery of M1 and M2 from urine was not changed.

Warfarin

In an open-label, two-way, crossover study, healthy subjects received 4 mg of glimepiride daily for 10 days. Single 25 mg doses of warfarin were administered six days before starting glimepiride and on Day 4 of glimepiride administration. The concomitant administration of glimepiride did not alter the pharmacokinetics of R- and S-warfarin enantiomers. No changes were observed in warfarin plasma protein binding. Glimepiride resulted in a statistically significant decrease in the pharmacodynamic response to warfarin. The reductions in mean area under the prothrombin time (PT) curve and maximum PT values during glimepiride treatment were 3.3% and 9.9%, respectively, and are unlikely to be clinically relevant.

Colesevelam

Concomitant administration of colesevelam and glimepiride resulted in reductions in glimepiride AUC0-∞ and Cmax of 18% and 8%, respectively. When glimepiride was administered 4 hours prior to colesevelam, there was not significant change in glimepiride AUC0-∞ and Cmax, -6% and 3%, respectively [see Dosage and Administration (2.4) and Drug Interactions (7.7)].

13 NONCLINICAL TOXICOLOGY

13.1 Carcinogenesis, Mutagenesis, Impairment of Fertility

No animal studies have been conducted with DUETACT. The following data are based on findings in studies performed with pioglitazone or glimepiride individually.

Pioglitazone

A two-year carcinogenicity study was conducted in male and female rats at oral doses up to 63 mg/kg (approximately 14 times the maximum recommended human oral dose of 45 mg based on mg/m^2). Drug-induced tumors were not observed in any organ except for the urinary bladder of male rats. Benign and/or malignant transitional cell neoplasms were observed in male rats at 4 mg/kg/day and above (approximately equal to the maximum recommended human oral dose based on mg/m^2). Urinary calculi with subsequent irritation and hyperplasia were postulated as the mechanism for bladder tumors observed in male rats. A two-year mechanistic study in male rats utilizing dietary acidification to reduce calculi formation was completed in 2009. Dietary acidification decreased but did not abolish the hyperplastic changes in the bladder. The presence of calculi exacerbated the hyperplastic response to pioglitazone but was not considered the primary cause of the hyperplastic changes.

The relevance to humans of the bladder findings in the male rat cannot be excluded.

A two-year carcinogenicity study was also conducted in male and female mice at oral doses up to 100 mg/kg/day (approximately 11 times the maximum recommended human oral dose based on mg/m^2). No drug-induced tumors were observed in any organ.

Pioglitazone hydrochloride was not mutagenic in a battery of genetic toxicology studies, including the Ames bacterial assay, a mammalian cell forward gene mutation assay (CHO/HPRT and AS52/XPRT), an in vitro cytogenetics assay using CHL cells, an unscheduled DNA synthesis assay, and an in vivo micronucleus assay.

No adverse effects upon fertility were observed in male and female rats at oral doses up to 40 mg/kg pioglitazone hydrochloride daily prior to and throughout mating and gestation (approximately nine times the maximum recommended human oral dose based on mg/m^2).

Glimepiride

Studies in rats at doses of up to 5000 parts per million (ppm) in complete feed (approximately 340 times the maximum recommended human dose, based on surface area) for 30 months showed no evidence of carcinogenesis. In mice, administration of glimepiride for 24 months resulted in an increase in benign pancreatic adenoma formation that was dose-related and was thought to be the result of chronic pancreatic stimulation. No adenoma formation in mice was observed at a dose of 320 ppm in complete feed, or 46 − 54 mg/kg body weight/day. This is about 35 times the maximum human recommended dose of 8 mg once daily based on surface area.

Glimepiride was non-mutagenic in a battery of in vitro and in vivo mutagenicity studies (Ames test, somatic cell mutation, chromosomal aberration, unscheduled DNA synthesis and mouse micronucleus test).

There was no effect of glimepiride on male mouse fertility in animals exposed up to 2500 mg/kg body weight (>1,700 times the maximum recommended human dose based on surface area). Glimepiride had no effect on the fertility of male and female rats administered up to 4000 mg/kg body weight (approximately 4,000 times the maximum recommended human dose based on surface area).

13.2 Animal Toxicology and/or Pharmacology

Pioglitazone

Heart enlargement has been observed in mice (100 mg/kg), rats (4 mg/kg and above), and dogs (3 mg/kg) treated orally with the pioglitazone hydrochloride component of DUETACT (approximately 11, one, and two times the maximum recommended human oral dose for mice, rats, and dogs, respectively, based on mg/m^2). In a one-year rat study, drug-related early death due to apparent heart dysfunction occurred at an oral dose of 160 mg/kg/day (approximately 35 times the maximum recommended human oral dose based on mg/m^2). Heart enlargement was seen in a 13-week study in monkeys at oral doses of 8.9 mg/kg and above (approximately four times the maximum recommended human oral dose based on mg/m^2), but not in a 52-week study at oral doses up to 32 mg/kg (approximately 13 times the maximum recommended human oral dose based on mg/m^2).

14 CLINICAL STUDIES

There have been no clinical efficacy studies conducted with DUETACT. However, the efficacy and safety of the separate components have been previously established. The coadministration of pioglitazone and a sulfonylurea, including glimepiride, has been evaluated for efficacy and safety in two clinical studies. These clinical studies established an added benefit of pioglitazone in glycemic control of patients with inadequately controlled type 2 diabetes while on sulfonylurea therapy. Bioequivalence of DUETACT with coadministered pioglitazone and glimepiride tablets was demonstrated at the 30 mg/2 mg and 30 mg/4 mg dosage strengths [see Clinical Pharmacology (12.3)].

Two clinical trials were conducted with pioglitazone in combination with a sulfonylurea. Both studies included patients with type 2 diabetes on any dose of a sulfonylurea, either alone or in combination with another antidiabetic agent. All other antidiabetic agents were withdrawn at least three weeks prior to starting study treatment.

In the first study, 560 patients were randomized to receive 15 mg or 30 mg of pioglitazone or placebo once daily for 16 weeks in addition to their current sulfonylurea regimen. Treatment with pioglitazone as add-on to sulfonylurea produced statistically significant improvements in HbA1c and FGP at endpoint compared to placebo add-on to sulfonylurea (Table 15).

Table 15. Glycemic Parameters in a 16-Week Placebo-Controlled, Add-on to Sulfonylurea Trial
 | Placebo + Sulfonylurea | Pioglitazone 15 mg + Sulfonylurea | Pioglitazone 30 mg + Sulfonylurea
Total Population
HbA1c (%) | N=181 | N=176 | N=182
Baseline (mean) | 9.9 | 10.0 | 9.9
Change from baseline (adjusted mean*) | 0.1 | -0.8 | -1.2
Difference from placebo + sulfonylurea (adjusted mean*) 95% Confidence Interval |  | -0.9† (-1.2, -0.6) | -1.3† (-1.6, -1.0)
Fasting Plasma Glucose (mg/dL) | N=182 | N=179 | N=186
Baseline (mean) | 236 | 247 | 239
Change from baseline (adjusted mean*) | 6 | -34 | -52
Difference from placebo + sulfonylurea (adjusted mean*) 95% Confidence Interval |  | -39† (-52, -27) | -58† (-70, -46)
*Adjusted for baseline, pooled center, and pooled center by treatment interaction
†p ≤0.05 versus placebo + sulfonylurea

In the second trial, 702 patients were randomized to receive 30 mg or 45 mg of pioglitazone once daily for 24 weeks in addition to their current sulfonylurea regimen. The mean reduction from baseline at Week 24 in HbA1c was 1.6% for the 30 mg dose and 1.7% for the 45 mg dose (see Table 16). The mean reduction from baseline at Week 24 in FPG was 52 mg/dL for the 30 mg dose and 56 mg/dL for the 45 mg dose.

The therapeutic effect of pioglitazone in combination with sulfonylurea was observed in patients regardless of the sulfonylurea dose.

Table 16. Glycemic Parameters in a 24-Week Add-on to Sulfonylurea Trial
 | Pioglitazone 30 mg + Sulfonylurea | Pioglitazone 45 mg + Sulfonylurea
Total Population
HbA1c (%) | N=340 | N=332
Baseline (mean) | 9.8 | 9.9
Change from baseline (adjusted mean*) | -1.6 | -1.7
Difference from 30 mg daily pioglitazone + sulfonylurea (adjusted mean*) (95% CI) |  | -0.1 (-0.4, 0.1)
Fasting Plasma Glucose (mg/dL) | N=338 | N=329
Baseline (mean) | 214 | 217
Change from baseline (adjusted mean*) | -52 | -56
Difference from 30 mg daily pioglitazone + sulfonylurea (adjusted mean*) (95% CI) |  | -5 (-12, 3)
95% CI = 95% confidence interval
*Adjusted for baseline, pooled center, and pooled center by treatment interaction

16 HOW SUPPLIED/STORAGE AND HANDLING

DUETACT is available in 30 mg pioglitazone plus 2 mg glimepiride or 30 mg pioglitazone plus 4 mg glimepiride tablets as follows:

30 mg/2 mg tablet: white to off-white, round, convex tablets, debossed with 4833G on one side and 30/2 on the other, available in:

NDC 64764-302-30 Bottles of 30

NDC 64764-302-90 Bottles of 90

30 mg/4 mg tablet: white to off-white, round, convex tablets, debossed with 4833G on one side and 30/4 on the other, available in:

NDC 64764-304-30 Bottles of 30

NDC 64764-304-90 Bottles of 90

Storage

Store at 25°C (77°F); excursions permitted to 15° to 30°C (59° to 86°F) [see USP Controlled Room Temperature]. Keep container tightly closed and protect from moisture and humidity.

17 PATIENT COUNSELING INFORMATION

See FDA-approved patient labeling (Medication Guide).

- Inform patients that DUETACT is not recommended for patients with symptoms of heart failure.
- Inform patients that patients with severe heart failure (NYHA Class III or IV) cannot start DUETACT as the risks exceed the benefits in such patients.
- It is important to instruct patients to adhere to dietary instructions and to have blood glucose and glycosylated hemoglobin tested regularly. During periods of stress such as fever, trauma, infection, or surgery, medication requirements may change and patients should be reminded to seek medical advice promptly. Patients should also be informed of the potential risks and advantages of DUETACT and of alternative modes of therapy.
- Tell patients to promptly report any sign of macroscopic hematuria or other symptoms such as dysuria or urinary urgency that develop or increase during treatment as these may be due to bladder cancer.
- Prior to initiation of DUETACT therapy, the risks of hypoglycemia, its symptoms and treatment, and conditions that predispose to its development should be explained to patients and responsible family members [see Warnings and Precautions (5.2)]. Combination therapy of DUETACT with other antihyperglycemic agents may also cause hypoglycemia.
- Patients who experience an unusually rapid increase in weight or edema or who develop shortness of breath or other symptoms of heart failure while on DUETACT should immediately report these symptoms to a physician.
- Tell patients to promptly stop taking DUETACT and seek immediate medical advice if there is unexplained nausea, vomiting, abdominal pain, fatigue, anorexia, or dark urine as these symptoms may be due to hepatotoxicity.
- Inform female patients that treatment with pioglitazone, like other thiazolidinediones may result in an unintended pregnancy in some premenopausal anovulatory females due to its effect on ovulation [see Use in Specific Populations (8.3)].
- Patients should be told to take a single dose of DUETACT once daily with the first main meal and instructed that any change in dosing should be made only if directed by their physician [see Dosage and Administration (2)].

Distributed by:
Takeda Pharmaceuticals America, Inc.
Cambridge, MA 02142

DUETACT is a registered trademark of Takeda Pharmaceutical Company Limited.

© 2025 Takeda Pharmaceuticals America, Inc. All rights reserved.

DTA007 R17

MEDICATION GUIDE
DUETACT® (doo-et' -ăct)
(pioglitazone and glimepiride) tablets

Read this Medication Guide carefully before you start taking DUETACT and each time you get a refill. There may be new information. This information does not take the place of talking with your doctor about your medical condition or your treatment. If you have any questions about DUETACT, ask your doctor or pharmacist.

What is the most important information I should know about DUETACT?
DUETACT can cause serious side effects, including new or worse heart failure.

- Pioglitazone, one of the medicines in DUETACT, can cause your body to keep extra fluid (fluid retention), which leads to swelling (edema) and weight gain. Extra body fluid can make some heart problems worse or lead to heart failure. Heart failure means your heart does not pump blood well enough
- Do not take DUETACT if you have severe heart failure
- If you have heart failure with symptoms (such as shortness of breath or swelling), even if these symptoms are not severe, DUETACT may not be right for you

Call your doctor right away if you have any of the following:

- swelling or fluid retention, especially in the ankles or legs
- shortness of breath or trouble breathing, especially when you lie down
- an unusually fast increase in weight
- unusual tiredness

DUETACT can have other serious side effects. See "What are the possible side effects of DUETACT?"

What is DUETACT?

DUETACT is a prescription medicine used with diet and exercise to improve blood sugar (glucose) control in adults with type 2 diabetes.

DUETACT contains 2 prescription diabetes medicines called pioglitazone (ACTOS®) and glimepiride, a sulfonylurea.

DUETACT is not for people with type 1 diabetes.

DUETACT is not for people with diabetic ketoacidosis (increased ketones in your blood or urine).

It is not known if DUETACT is safe and effective in children under the age of 18. DUETACT is not recommended for use in children.

Who should not take DUETACT?

See "What is the most important information I should know about DUETACT?"

Do not take DUETACT if you:

- have severe heart failure
- are allergic to any of the ingredients in DUETACT. See the end of this Medication Guide for a complete list of ingredients in DUETACT
- have a condition called diabetic ketoacidosis. Diabetic ketoacidosis should be treated with insulin

Talk to your doctor before taking DUETACT if you have any of these conditions.

What should I tell my doctor before taking DUETACT?

Before you take DUETACT, tell your doctor if you:

- have heart failure
- have kidney problems
- have type 1 ("juvenile") diabetes or had diabetic ketoacidosis
- have a type of diabetic eye disease that causes swelling in the back of the eye (macular edema)
- have liver problems
- have or have had cancer of the bladder
- are pregnant or plan to become pregnant. It is not known if DUETACT can harm your unborn baby. Talk to your doctor if you are pregnant or plan to become pregnant about the best way to control your blood glucose levels while pregnant
- are a premenopausal woman (before the "change of life"), who does not have periods regularly or at all. DUETACT may increase your chance of becoming pregnant. Talk to your doctor about birth control choices while taking DUETACT. Tell your doctor right away if you become pregnant while taking DUETACT
- are breastfeeding or plan to breastfeed. It is not known if DUETACT passes into your milk and if it can harm your baby. Talk to your doctor about the best way to control your blood glucose levels while breastfeeding
- have G6PD deficiency (an inherited condition where you don't produce enough of the enzyme (G6PD). Taking glimepiride, one of the medicines in DUETACT, with this condition may cause your red blood cells to be destroyed too quickly (hemolytic anemia)

Tell your doctor about all the medicines you take including prescription and over the counter medicines, vitamins, and herbal supplements.

DUETACT and some of your other medicines can affect each other. You may need to have your dose of DUETACT or certain other medicines changed.

Know the medicines you take. Keep a list of your medicines and show it to your doctor and pharmacist before you start a new medicine. They will tell you if it is okay to take DUETACT with other medicines.

How should I take DUETACT?

- Take DUETACT exactly as your doctor tells you to take it
- Your doctor may change your dose of DUETACT. Do not change your dose unless your doctor tells you to
- DUETACT may be prescribed alone or with other diabetes medicines. This will depend on how well your blood sugar is controlled
- Take DUETACT one time each day with the first main meal
- If you take colesevelam, a medicine used to lower your cholesterol, take your DUETACT at least 4 hours before you take your colesevelam.
- If you miss a dose of DUETACT, take your next dose as prescribed unless your doctor tells you differently. Do not take two doses at one time the next day
- If you take too much DUETACT, call your doctor or go to the nearest hospital emergency room right away
- If your body is under stress such as from a fever, infection, accident, or surgery, the dose of your diabetes medicines may need to be changed. Call your doctor right away
- Stay on your diet and exercise programs and test your blood sugar regularly while taking DUETACT
- Your doctor should do certain blood tests before you start and while you take DUETACT
- Your doctor should also do hemoglobin A1C testing to check how well your blood sugar is controlled with DUETACT
- Your doctor should check your eyes regularly while you take DUETACT

What are the possible side effects of DUETACT?

DUETACT may cause serious side effects including:

- See "What is the most important information I should know about DUETACT?"
- low blood sugar (hypoglycemia). This can happen if you skip meals, if you also use another medicine that lowers blood sugar, or if you have certain medical problems. Lightheadedness, dizziness, shakiness, or hunger may happen if your blood sugar is too low. Severe low blood sugar can cause unconsciousness (passing out), seizures, and death. Call your doctor if low blood sugar levels are a problem for you
- liver problems. Call your doctor right away if you have:
  - nausea or vomiting
  - stomach pain
  - unusual or unexplained tiredness
  - loss of appetite
  - dark urine
  - yellowing of your skin or the whites of your eyes
- bladder cancer. There may be an increased chance of having bladder cancer when you take DUETACT. You should not take DUETACT if you are receiving treatment for bladder cancer. Tell your doctor right away if you have any of the following symptoms of bladder cancer:
  - blood or a red color in your urine
  - an increased need to urinate
  - pain while you urinate
- broken bones (fractures). Usually in the hand, upper arm, or foot in women. Talk to your doctor for advice on how to keep your bones healthy.
- diabetic eye disease with swelling in the back of the eye (macular edema). Tell your doctor right away if you have any changes in your vision. Your doctor should check your eyes regularly
- release of an egg from an ovary in a woman (ovulation) leading to pregnancy. Ovulation may happen when premenopausal women who do not have regular monthly periods take DUETACT. This can increase your chance of getting pregnant

The most common side effects of DUETACT include:

- cold-like symptoms (upper respiratory tract infection)
- headache
- sinus infection
- diarrhea
- nausea
- muscle pain
- sore throat

Tell your doctor if you have any side effect that bothers you or that does not go away. These are not all the side effects of DUETACT. For more information, ask your doctor or pharmacist.

Call your doctor for medical advice about side effects. You may report side effects to FDA at 1-800-FDA-1088.

How should I store DUETACT?

- Store DUETACT at 68°F to 77°F (20°C to 25°C). Keep DUETACT in the original container to protect from light
- Keep the DUETACT bottle tightly closed and keep tablets dry
- Keep DUETACT and all medicines out of the reach of children

General information about the safe and effective use of DUETACT

Medicines are sometimes prescribed for purposes other than those listed in a Medication Guide. Do not use DUETACT for a condition for which it was not prescribed. Do not give DUETACT to other people, even if they have the same symptoms you have. It may harm them.

This Medication Guide summarizes the most important information about DUETACT. If you would like more information, talk with your doctor. You can ask your doctor or pharmacist for information about DUETACT that is written for healthcare professionals. For more information, go to www.duetact.com or call 1-877-825-3327.

What are the ingredients in DUETACT?

Active ingredients: pioglitazone and glimepiride

Inactive ingredients: croscarmellose sodium, lactose monohydrate, magnesium stearate, hydroxypropyl cellulose, polysorbate 80, and microcrystalline cellulose

This Medication Guide has been approved by the U.S. Food and Drug Administration.

Distributed by:

Takeda Pharmaceuticals America, Inc.

Cambridge, MA 02142

Revised: March 2025

DUETACT and ACTOS are registered trademarks of Takeda Pharmaceutical Company Limited.

© 2025 Takeda Pharmaceuticals America, Inc. All rights reserved.

DTA007 R17

PRINCIPAL DISPLAY PANEL - 30 mg/2 mg Tablet Bottle Label

NDC 64764-302-30
30 Tablets

duetact®
pioglitazone 30 mg and
glimepiride 2 mg tablets

Each tablet contains pioglitazone
hydrochloride equivalent to 30 mg
pioglitazone and 2 mg glimepiride.

Dispense with Medication Guide
available in package insert or at
www.duetact.com

Takeda
Rx Only

PRINCIPAL DISPLAY PANEL - 30 mg/4 mg Tablet Bottle Label

NDC 64764-304-30
30 Tablets

duetact®
pioglitazone 30 mg and
glimepiride 4 mg tablets

Each tablet contains pioglitazone
hydrochloride equivalent to 30 mg
pioglitazone and 4 mg glimepiride.

Dispense with Medication Guide
available in package insert or at
www.duetact.com

Takeda
Rx Only